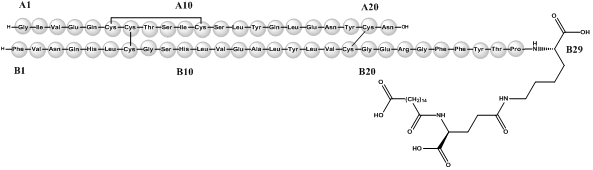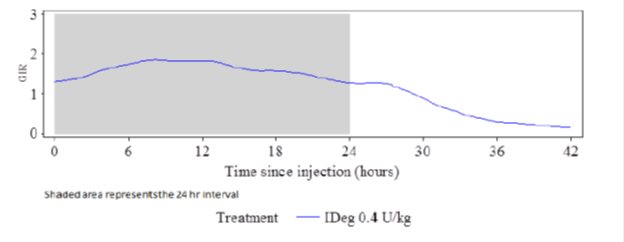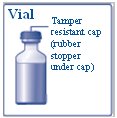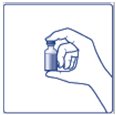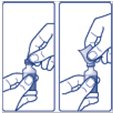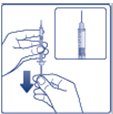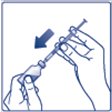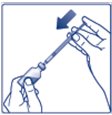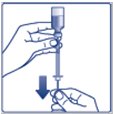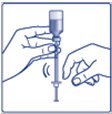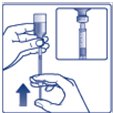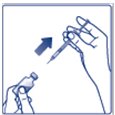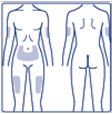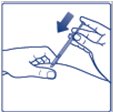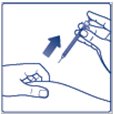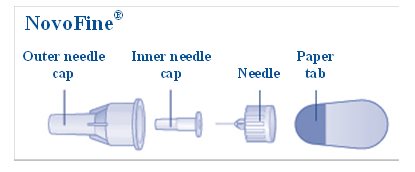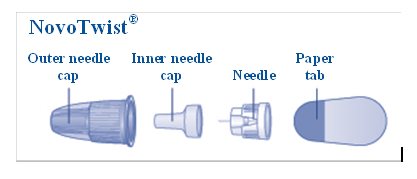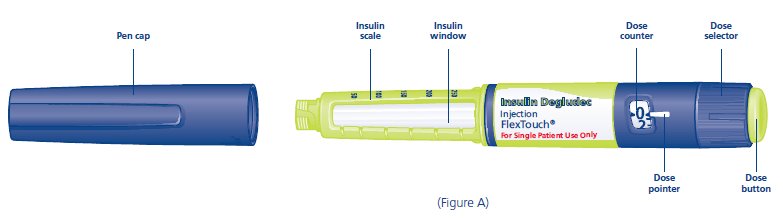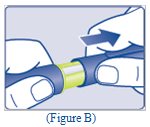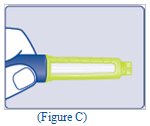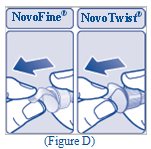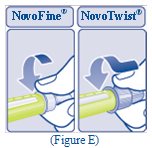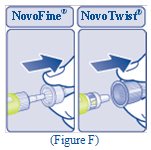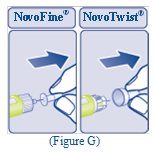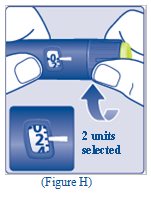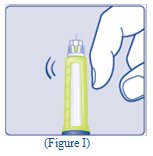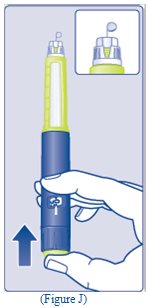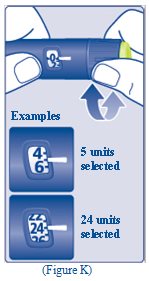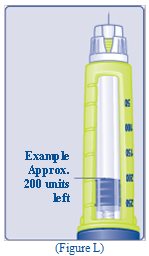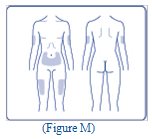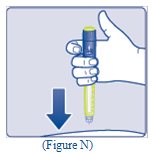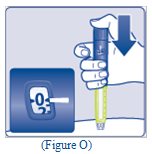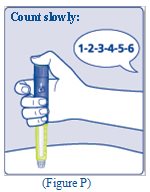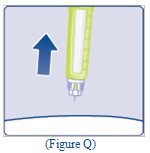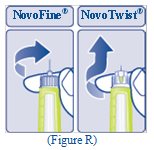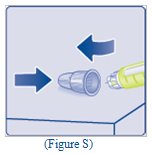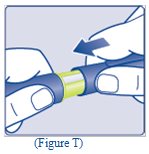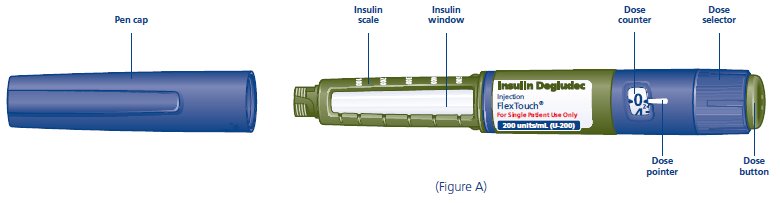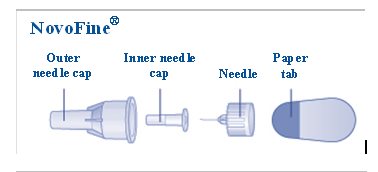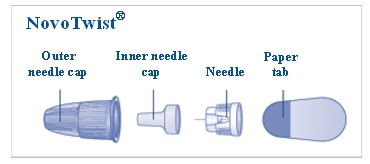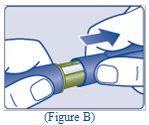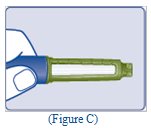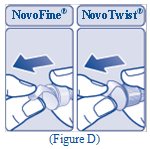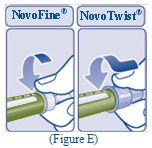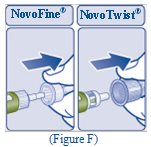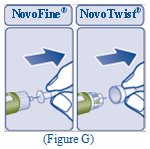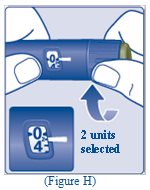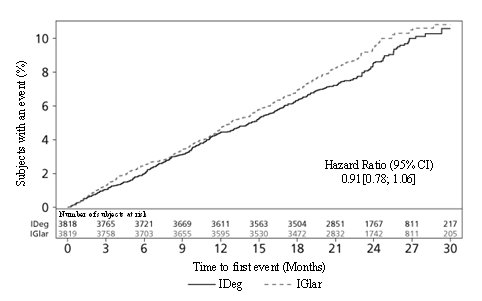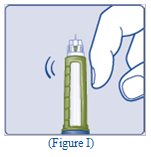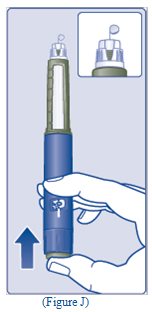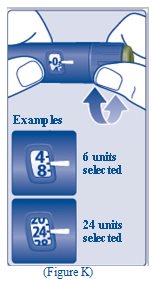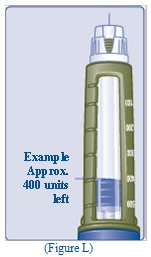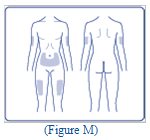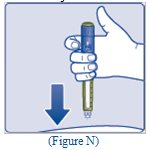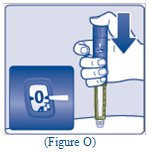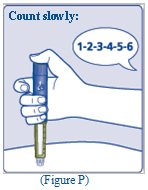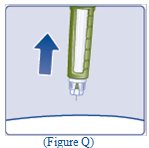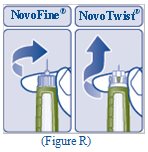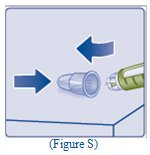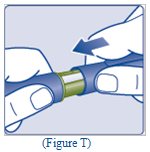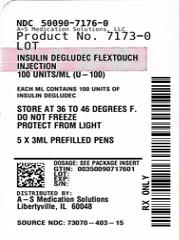 DRUG LABEL: Insulin Degludec
NDC: 50090-7176 | Form: INJECTION, SOLUTION
Manufacturer: A-S Medication Solutions
Category: prescription | Type: HUMAN PRESCRIPTION DRUG LABEL
Date: 20240603

ACTIVE INGREDIENTS: INSULIN DEGLUDEC 100 U/1 mL
INACTIVE INGREDIENTS: GLYCERIN 19.6 mg/1 mL; PHENOL 1.50 mg/1 mL; METACRESOL 1.72 mg/1 mL; ZINC 32.7 ug/1 mL; WATER; HYDROCHLORIC ACID; SODIUM HYDROXIDE

HIGHLIGHTS OF PRESCRIBING INFORMATION

These highlights do not include all the information needed to use INSULIN DEGLUDEC safely and effectively. See full prescribing information for INSULIN DEGLUDEC.
INSULIN DEGLUDEC injection, for subcutaneous use
Initial U.S. Approval: 2015
This product is Tresiba (insulin degludec).

1 INDICATIONS AND USAGE

Insulin Degludec is a long-acting human insulin analog indicated to improve glycemic control in patients 1 year of age and older with diabetes mellitus (1).

Limitations of Use:

- Not recommended for the treatment of diabetic ketoacidosis.

2 DOSAGE AND ADMINISTRATION

- See Full Prescribing Information for important administration instructions (2.1).
- Inject Insulin Degludec subcutaneously into the thigh, upper arm, or abdomen (2.1).
- Rotate injection sites to reduce risk of lipodystrophy and localized cutaneous amyloidosis (2.1).
- For pediatric patients requiring less than 5 units of Insulin Degludec each day, use an Insulin Degludec U-100 vial (2.1).
- In adults, inject subcutaneously once daily at any time of day (2.2).
- In pediatric patients inject subcutaneously once daily at the same time every day (2.2).
- Individualize dose based on type of diabetes, metabolic needs, blood glucose monitoring results and glycemic control goal (2.2).
- The recommended days between dose increases are 3 to 4 days (2.2).
- See Full Prescribing Information for recommended starting dose in insulin naïve patients and patients already on insulin therapy (2.3, 2.4).

3 DOSAGE FORMS AND STRENGTHS

Injection: Available as:

- 100 units/mL (U-100): 3 mL single-patient-use FlexTouch® prefilled pen (3).
- 100 units/mL (U-100): 10 mL multiple-dose vial (3).
- 200 units/mL (U-200): 3 mL single-patient-use FlexTouch® prefilled pen (3).

4 CONTRAINDICATIONS

- During episodes of hypoglycemia (4).
- Hypersensitivity to insulin degludec or any of the excipients in Insulin Degludec (4).

5 WARNINGS AND PRECAUTIONS

- Never share an Insulin Degludec FlexTouch pen, insulin syringe, or needle between patients, even if the needle is changed (5.1).
- Hyperglycemia or hypoglycemia with changes in insulin regimen: Make changes to a patient’s insulin regimen (e.g., insulin strength, manufacturer, type, injection site or method of administration) under close medical supervision with increased frequency of blood glucose monitoring (5.2).
- Hypoglycemia: May be life-threatening. Increase monitoring with changes to: insulin dosage, concomitant drugs, meal pattern, physical activity; and in patients with renal impairment or hepatic impairment or hypoglycemia unawareness (5.3, 5.4, 6.1).
- Hypoglycemia due to medication errors: Accidental mix-ups between insulin products can occur. Instruct patients to check insulin labels before injection. DO NOT transfer Insulin Degludec from the Insulin Degludec pen into a syringe for administration as overdosage and severe hypoglycemia can result (5.4).
- Hypersensitivity reactions: Severe, life-threatening, generalized allergy, including anaphylaxis, can occur. Discontinue Insulin Degludec, monitor and treat if indicated (5.5).
- Hypokalemia: May be life-threatening. Monitor potassium levels in patients at risk for hypokalemia and treat if indicated (5.6).
- Fluid retention and heart failure with concomitant use of Thiazolidinediones (TZDs): Observe for signs and symptoms of heart failure; consider dosage reduction or discontinuation if heart failure occurs (5.7).

6 ADVERSE REACTIONS

Adverse reactions commonly associated with Insulin Degludec are:

- hypoglycemia, allergic reactions, injection site reactions, lipodystrophy, pruritus, rash, edema and weight gain (6.1).

To report SUSPECTED ADVERSE REACTIONS, contact Novo Nordisk Pharma, Inc. at 1-800-727-6500 or FDA at 1-800-FDA-1088 or www.fda.gov/medwatch.

7 DRUG INTERACTIONS

- Drugs that Affect Glucose Metabolism: Adjustment of insulin dosage may be needed. (7)
- Antiadrenergic Drugs (e.g., beta-blockers, clonidine, guanethidine, and reserpine): Signs and symptoms of hypoglycemia may be reduced or absent. (5.3, 7)

FULL PRESCRIBING INFORMATION

1 INDICATIONS AND USAGE

Insulin Degludec is indicated to improve glycemic control in patients 1 year of age and older with diabetes mellitus.

Limitations of Use

- Not recommended for the treatment of diabetic ketoacidosis.

2 DOSAGE AND ADMINISTRATION

2.1 Important Administration Instructions

- Always check insulin labels before administration. This product is Tresiba (insulin degludec) [see Warnings and Precautions (5.4)].
- Inspect visually for particulate matter and discoloration. Only use Insulin Degludec if the solution appears clear and colorless.
- Inject Insulin Degludec subcutaneously into the thigh, upper arm, or abdomen.
- Rotate injection sites within the same region from one injection to the next to reduce the risk of lipodystrophy and localized cutaneous amyloidosis. Do not inject into areas of lipodystrophy or localized cutaneous amyloidosis [see Warnings and Precautions (5.2), Adverse Reactions (6.1, 6.3)].
- During changes to a patient’s insulin regimen, increase the frequency of blood glucose monitoring [see Warnings and Precautions (5.2)].
- For pediatric patients requiring less than 5 units of Insulin Degludec each day, use the Insulin Degludec U-100 vial.
- DO NOT administer Insulin Degludec intravenously or in an insulin infusion pump.
- DO NOT dilute or mix Insulin Degludec with any other insulin or solution.
- DO NOT transfer Insulin Degludec from the Insulin Degludec FlexTouch pen into a syringe for administration [see Warnings and Precautions (5.4)].
- Use Insulin Degludec FlexTouch pens with caution in patients with visual impairment that may rely on audible clicks to dial their dose.

2.2 General Dosing Instructions

- Insulin Degludec is available in 2 concentrations (U-100 and U-200):
  - Insulin Degludec U-100 is available, as a single-patient use FlexTouch pen and multiple-dose vial.
    - The FlexTouch pen delivers doses in 1 unit increments and can deliver up to 80 units in a single injection.
  - Insulin Degludec U-200 is available as a single-patient-use FlexTouch pen.
    - The FlexTouch pen delivers doses in 2 unit increments and can deliver up to 160 units in a single injection.
- DO NOT perform dose conversion when using the Insulin Degludec U-100 or U-200 FlexTouch pens. The dose window shows the number of insulin units to be delivered and no conversion is needed.
- In adults, inject Insulin Degludec subcutaneously once-daily at any time of day.
- In pediatric patients inject Insulin Degludec subcutaneously once-daily at the same time every day.
- Individualize and titrate the dose of Insulin Degludec based on the patient’s metabolic needs, blood glucose monitoring results, and glycemic control goal.
- The recommended days between dose increases are 3 to 4 days.
- Dose adjustments may be needed with changes in physical activity, changes in meal patterns (i.e., macronutrient content or timing of food intake), changes in renal or hepatic function or during acute illness to minimize the risk of hypoglycemia or hyperglycemia [see Warnings and Precautions (5.3)].
- For adult patients, instruct patients who miss a dose of Insulin Degludec to inject their daily dose during waking hours upon discovering the missed dose. Instruct patients to ensure that at least 8 hours have elapsed between consecutive Insulin Degludec injections.
- For pediatric patients, instruct patients who miss a dose of Insulin Degludec to contact their healthcare provider for guidance and to monitor blood glucose levels more frequently until the next scheduled Insulin Degludec dose.
- In patients with type 1 diabetes, Insulin Degludec must be used concomitantly with short-acting insulin.

2.3 Starting Dose in Insulin Naïve Patients

Recommended Starting Dosage in Patients with Type 1 Diabetes Mellitus:

The recommended starting dose of Insulin Degludec in insulin naïve patients with type 1 diabetes is approximately one-third to one-half of the total daily insulin dose. The remainder of the total daily insulin dose should be administered as a short-acting insulin and divided between each daily meal. As a general rule, 0.2 to 0.4 units of insulin per kilogram of body weight can be used to calculate the initial total daily insulin dose in insulin naïve patients with type 1 diabetes.

Recommended Starting Dosage in Patients with Type 2 Diabetes Mellitus:

The recommended starting dose of Insulin Degludec in insulin naïve patients with type 2 diabetes mellitus is 10 units once daily.

2.4 Switching to Insulin Degludec from Other Insulin Therapies

Dosage adjustments are recommended to lower the risk of hypoglycemia when switching patients to Insulin Degludec from another insulin therapy [see Warnings and Precautions (5.3)].

Adults with Type 1 or Type 2 Diabetes Mellitus:

Start Insulin Degludec at the same unit dose as the total daily long or intermediate-acting insulin unit dose.

Pediatric Patients 1 Year of Age and Older with Type 1 or Type 2 Diabetes Mellitus:

Start Insulin Degludec at 80% of the total daily long or intermediate-acting insulin unit dose to minimize the risk of hypoglycemia [see Warnings and Precautions (5.2)].

3 DOSAGE FORMS AND STRENGTHS

Injection: Available as a clear and colorless solution:

- 100 units/mL (U-100): 3 mL single-patient-use FlexTouch prefilled pen
- 100 units/mL (U-100): 10 mL multiple-dose vial
- 200 units/mL (U-200): 3 mL single-patient-use FlexTouch prefilled pen

4 CONTRAINDICATIONS

Insulin Degludec is contraindicated:

- During episodes of hypoglycemia [see Warnings and Precautions (5.3)].
- In patients with hypersensitivity to insulin degludec or any of the excipients in Insulin Degludec [see Warnings and Precautions (5.5)].

5 WARNINGS AND PRECAUTIONS

5.1 Never Share an Insulin Degludec FlexTouch Pen, Needle, or Insulin Syringe Between Patients

Insulin Degludec FlexTouch disposable prefilled pens should never be shared between patients, even if the needle is changed. Patients using Insulin Degludec vials should never share needles or syringes with another person. Sharing poses a risk for transmission of blood-borne pathogens.

5.2 Hyperglycemia or Hypoglycemia with Changes in Insulin Regimen

Changes in an insulin regimen (e.g., insulin strength, manufacturer, type, injection site or method of administration) may affect glycemic control and predispose to hypoglycemia [see Warnings and Precautions (5.3)] or hyperglycemia. Repeated insulin injections into areas of lipodystrophy or localized cutaneous amyloidosis have been reported to result in hyperglycemia; and a sudden change in the injection site (to an unaffected area) has been reported to result in hypoglycemia [see Adverse Reactions (6.1, 6.3)].

Make any changes to a patient’s insulin regimen under close medical supervision with increased frequency of blood glucose monitoring. Advise patients who have repeatedly injected into areas of lipodystrophy or localized cutaneous amyloidosis to change the injection site to unaffected areas and closely monitor for hypoglycemia. For patients with type 2 diabetes, adjustments in concomitant anti-diabetic treatment may be needed [see Dosage and Administration (2.4)].

5.3 Hypoglycemia

Hypoglycemia is the most common adverse reaction of insulin, including Insulin Degludec [see Adverse Reactions (6.1)]. Severe hypoglycemia can cause seizures, may be life-threatening or cause death. Hypoglycemia can impair concentration ability and reaction time; this may place the patient and others at risk in situations where these abilities are important (e.g., driving or operating other machinery). Insulin Degludec, or any insulin, should not be used during episodes of hypoglycemia [see Contraindications (4)].

Hypoglycemia can happen suddenly and symptoms may differ in each patient and change over time in the same patient. Symptomatic awareness of hypoglycemia may be less pronounced in patients with longstanding diabetes, in patients with diabetic neuropathy, using drugs that block the sympathetic nervous system (e.g., beta-blockers) [see Drug Interactions (7)], or who experience recurrent hypoglycemia.

The long-acting effect of Insulin Degludec may delay recovery from hypoglycemia compared to shorter-acting insulins.

Risk Factors for Hypoglycemia

The risk of hypoglycemia generally increases with intensity of glycemic control. The risk of hypoglycemia after an injection is related to the duration of action of the insulin [see Clinical Pharmacology (12.2)] and, in general, is highest when the glucose lowering effect of the insulin is maximal. As with all insulins, the glucose lowering effect time course of Insulin Degludec may vary among different patients or at different times in the same patients and depends on many conditions, including the area of injection as well as the injection site blood supply and temperature.

Other factors which may increase the risk of hypoglycemia include changes in meal pattern (e.g., macronutrient content or timing of meals), changes in level of physical activity, or changes to concomitant drugs [see Drug Interactions (7)]. Patients with renal or hepatic impairment may be at higher risk of hypoglycemia [see Use in Specific Populations (8.6, 8.7)].

Risk Mitigation Strategies for Hypoglycemia

Patients and caregivers must be educated to recognize and manage hypoglycemia. Self-monitoring of blood glucose plays an essential role in the prevention and management of hypoglycemia. In patients at higher risk for hypoglycemia and patients who have reduced symptomatic awareness of hypoglycemia, increased frequency of blood glucose monitoring is recommended.

5.4 Hypoglycemia Due to Medication Errors

Accidental mix-ups between insulin products, have been reported. To avoid medication errors between Insulin Degludec and other insulins, instruct patients to always check the insulin label before each injection.

To avoid dosing errors and potential overdose, never use a syringe to remove Insulin Degludec from the Insulin Degludec FlexTouch disposable insulin prefilled pen [see Dosage and Administration (2.1) and Warnings and Precautions (5.3)].

5.5 Hypersensitivity Reactions

Severe, life-threatening, generalized allergy, including anaphylaxis, can occur with insulins, including Insulin Degludec [see Adverse Reactions (6.1)]. If hypersensitivity reactions occur, discontinue Insulin Degludec; treat per standard of care and monitor until symptoms and signs resolve. Insulin Degludec is contraindicated in patients who have had hypersensitivity reactions to insulin degludec or any of the excipients.

5.6 Hypokalemia

All insulins, including Insulin Degludec, cause a shift in potassium from the extracellular to intracellular space, possibly leading to hypokalemia. Untreated hypokalemia may cause respiratory paralysis, ventricular arrhythmia, and death. Monitor potassium levels in patients at risk for hypokalemia if indicated (e.g., patients using potassium-lowering medications, patients taking medications sensitive to serum potassium concentrations).

5.7 Fluid Retention and Congestive Heart Failure with Concomitant Use of a PPAR Gamma Agonist

Thiazolidinediones (TZDs), which are peroxisome proliferator-activated receptor (PPAR)-gamma agonists can cause dose related fluid retention, when used in combination with insulin. Fluid retention may lead to or exacerbate congestive heart failure. Patients treated with insulin, including Insulin Degludec and a PPAR-gamma agonist should be observed for signs and symptoms of congestive heart failure. If congestive heart failure develops, it should be managed according to current standards of care and discontinuation or dose reduction of the PPAR-gamma agonist must be considered.

6 ADVERSE REACTIONS

The following adverse reactions are also discussed elsewhere:

- Hypoglycemia [see Warnings and Precautions (5.3)]
- Hypoglycemia due to Medication errors [see Warnings and Precautions (5.4)]
- Hypersensitivity reactions [see Warnings and Precautions (5.5)]
- Hypokalemia [see Warnings and Precautions (5.6)]

6.1 Clinical Trial Experience

Because clinical trials are conducted under widely varying conditions, adverse reaction rates observed in the clinical trials of a drug cannot be directly compared to rates in the clinical trials of another drug and may not reflect the rates observed in practice.

The safety of Insulin Degludec in subjects with type 1 diabetes or type 2 diabetes was evaluated in nine trials of 6-12 month duration in adults and in one trial of 12-month duration in pediatric patients 1 year of age and older with type 1 diabetes. The cardiovascular safety of Insulin Degludec was evaluated in one double-blinded, event-driven trial of 2-year median duration in patients with type 2 diabetes at high risk of cardiovascular events [see Clinical Studies (14)].

The data in Table 1 reflect the exposure of 1102 adults with type 1 diabetes to Insulin Degludec with a mean exposure duration to Insulin Degludec of 34 weeks in three open-label trials; Study A, B and C [see Clinical Studies (14.1)]. The mean age was 43 years and 1% were older than 75 years. Fifty-seven percent were male, 81% were White, 2% were Black or African American and 4% were Hispanic. The mean body mass index (BMI) was 26 kg/m^2. The mean duration of diabetes was 18 years and the mean HbA1c at baseline was 7.8%. A history of neuropathy, ophthalmopathy, nephropathy and cardiovascular disease at baseline was reported in 11%, 16%, 7% and 0.5% respectively. The mean eGFR at baseline was 87 mL/min/1.73 m^2 and 7% of the patients had an eGFR less than 60 mL/min/1.73 m^2.

The data in Table 2 reflect the exposure of 2713 adults with type 2 diabetes to Insulin Degludec with a mean exposure duration to Insulin Degludec of 36 weeks in six open-label trials; Study D, E, F, G, H and I [see Clinical Studies (14.3)]. The mean age was 58 years and 3% were older than 75 years. Fifty-eight percent were male, 71% were White, 7% were Black or African American and 13% were Hispanic. The mean BMI was 30 kg/m^2. The mean duration of diabetes was 11 years and the mean HbA1c at baseline was 8.3%. A history of neuropathy, ophthalmopathy, nephropathy and cardiovascular disease at baseline was reported for 14%, 10%, 6% and 0.6% of participants respectively. At baseline, the mean eGFR was 83 mL/min/1.73 m^2 and 9% had an eGFR less than 60 mL/min/1.73 m^2.

Common adverse reactions (excluding hypoglycemia) occurring in Insulin Degludec treated subjects during clinical trials in adult patients with type 1 diabetes mellitus and adults with type 2 diabetes mellitus are listed in Table 1 and Table 2, respectively. Common adverse reactions were defined as reactions occurring in ≥5% of the population studied. Hypoglycemia is not shown in these tables but discussed in a dedicated subsection below.

174 pediatric patients 1 year of age and older with type 1 diabetes were exposed to Insulin Degludec with a mean exposure to Insulin Degludec of 48 weeks. The mean age was 10 years: 25% were ages 1-5 years, 40% were ages 6-11 years, and 35% were ages 12-17 years. 55% were male, 78% were White, 3% were Black or African American and 4% were Hispanic. The mean body mass index (BMI) was 18.7 kg/m^2. The mean duration of diabetes was 3.9 years and the mean HbA1c at baseline was 8.2%. Common adverse reactions in Insulin Degludec treated pediatric patients with type 1 diabetes mellitus were similar to the adverse reactions listed in Table 1.

Table 1: Adverse Reactions Occurring in ≥5% of Insulin Degludec-Treated Adult Patients with Type 1 Diabetes Mellitus

Adverse Reaction | Insulin Degludec; (N=1,102)
Nasopharyngitis | 23.9 %
Upper respiratory tract infection | 11.9 %
Headache | 11.8 %
Sinusitis | 5.1 %
Gastroenteritis | 5.1 %

Table 2: Adverse Reactions Occurring in ≥5% of Insulin Degludec-Treated Adult Patients with Type 2 Diabetes Mellitus

Adverse Reaction | Insulin Degludec; (N=2,713)
Nasopharyngitis | 12.9 %
Headache | 8.8 %
Upper respiratory tract infection | 8.4 %
Diarrhea | 6.3 %

Hypoglycemia

Hypoglycemia was the most commonly observed adverse reaction in patients treated with Insulin Degludec. The rates of reported hypoglycemia depended on the definition of hypoglycemia used, diabetes type, insulin dose, intensity of glucose control, background therapies, and other intrinsic and extrinsic patient factors. For these reasons, comparing rates of hypoglycemia in clinical trials for Insulin Degludec with the incidence of hypoglycemia for other products may be misleading and also, may not be representative of hypoglycemia rates that will occur in clinical practice.

In the open-label adult clinical trials of patients with type 1 and type 2 diabetes, and in the open-label pediatric clinical trial of patients with type 1 diabetes, percentages of adult and pediatric patients with type 1 diabetes randomized to Insulin Degludec who experienced at least one episode of hypoglycemia in clinical trials [see Clinical Studies (14)] and adults with type 2 diabetes are shown in Tables 3 and 4, respectively.

Severe hypoglycemia in the open-label trials with adult patients was defined as an episode requiring assistance of another person to actively administer carbohydrate, glucagon, or other resuscitative actions. Severe hypoglycemia in the pediatric trial was defined as an altered mental status where the child could not assist in his own care, was semiconscious or unconscious, or in a coma ± convulsions and may require parenteral therapy (glucagon or intravenous glucose). A hypoglycemia episode was defined as a severe hypoglycemia episode or an episode where a laboratory or a self-measured glucose calibrated to plasma was less than 56 mg/dL or where a whole blood glucose was less than 50 mg/dL (i.e., with or without the presence of hypoglycemic symptoms).

Table 3: Percent (%) of Type 1 Diabetes Patients Experiencing at Least One Episode of Severe Hypoglycemia or Hypoglycemia§ on Insulin Degludec in Open-Label Adult and Pediatric Clinical Trials

 | Study A Adults + insulin aspart 52 weeks | Study B Adults + insulin aspart 26 weeks | Study C Adults + insulin aspart 26 weeks |  | Study J Pediatrics + insulin aspart 52 weeks
 | Insulin Degludec (N=472) | Insulin Degludec (N=301) | Insulin Degludec at the same time each day (N=165) | Insulin Degludec at alternating times (N=164) | Insulin Degludec (N=174)
Severe hypoglycemia*
Percent of patients | 12.3% | 10.6% | 12.7% | 10.4% | 17.8%
Hypoglycemia§
Percent of patients | 95.6% | 93.0% | 99.4% | 93.9% | 98.3%

*Severe hypoglycemia in pediatric patients: an episode with altered mental status, where the child could not assist in his own care, was semiconscious or unconscious, or in a coma ± convulsions and may require parenteral therapy (glucagon or intravenous glucose).

§Hypoglycemia: a severe hypoglycemia episode or an episode where a laboratory or a self-measured glucose calibrated to plasma was less than 56 mg/dL or where a whole blood glucose was less than 50 mg/dL (i.e., with or without the presence of hypoglycemic symptoms).

Table 4: Percent (%) of Patients with Type 2 Diabetes Experiencing at Least One Episode of Severe Hypoglycemia or Hypoglycemia§ on Insulin Degludec in Open-Label Adult Clinical Trials

 | Study D + 1-2 OADs* insulin naïve 52 weeks | Study E + 1-2 OADs* insulin naïve 26 weeks | Study F ± 1-3 OADs* insulin naïve 26 weeks | Study G T2DM ± 0-3 OADs* 26 weeks |  | Study H T2DM ± 0-2 OADs* + insulin aspart 52 weeks | Study I T2DM ± 1-2 OADs* insulin naïve 26 weeks
 | Insulin Degludec (N=766) | Insulin Degludec (N=228) | Insulin Degludec (N=284) | Insulin Degludec (N=226) | Insulin Degludec (alternating time) (N=230) | Insulin Degludec (N=753) | Insulin Degludec (N=226)
Severe Hypoglycemia
Percent of patients | 0.3% | 0 | 0 | 0.9% | 0.4% | 4.5% | 0.4%
Hypoglycemia§
Percent of patients | 46.5% | 28.5% | 50% | 43.8% | 50.9% | 80.9% | 42.5%

*OAD: oral antidiabetic agent, §Hypoglycemia: a severe hypoglycemia episode or an episode where a laboratory or a self-measured glucose calibrated to plasma was less than 56 mg/dL or where a whole blood glucose was less than 50 mg/dL (i.e., with or without the presence of hypoglycemic symptoms).

Hypersensitivity Reactions

Severe, life-threatening, generalized allergy, including anaphylaxis, generalized skin reactions, angioedema, bronchospasm, hypotension, and shock have occurred with insulin, including Insulin Degludec and may be life threatening. Hypersensitivity (manifested with swelling of tongue and lips, diarrhea, nausea, tiredness, and itching) and urticaria were reported in 0.9% of patients treated with Insulin Degludec.

Lipodystrophy

Long-term use of insulin, including Insulin Degludec, can cause lipodystrophy at the site of repeated insulin injections. Lipodystrophy includes lipohypertrophy (thickening of adipose tissue) and lipoatrophy (thinning of adipose tissue) and may affect insulin absorption [see Dosage and Administration (2.1)]. In the clinical program, lipodystrophy, lipohypertrophy, or lipoatrophy was reported in 0.3% of patients treated with Insulin Degludec.

Injection Site Reactions

Patients taking Insulin Degludec may experience injection site reactions, including injection site hematoma, pain, hemorrhage, erythema, nodules, swelling, discoloration, pruritus, warmth, and injection site mass. In the clinical program, injection site reactions occurred in 3.8% of patients treated with Insulin Degludec.

Weight Gain

Weight gain can occur with insulin therapy, including Insulin Degludec, and has been attributed to the anabolic effects of insulin. In the clinical program after 52 weeks of treatment, patients with type 1 diabetes treated with Insulin Degludec gained an average of 1.8 kg and patients with type 2 diabetes treated with Insulin Degludec gained an average of 3.0 kg.

Peripheral Edema

Insulin Degludec may cause sodium retention and edema. In the clinical program, peripheral edema occurred in 0.9% of patients with type 1 diabetes mellitus and 3.0% of patients with type 2 diabetes mellitus treated with Insulin Degludec.

6.2 Immunogenicity

As with all therapeutic proteins, insulin administration may cause anti-insulin antibodies to form. The detection of antibody formation is highly dependent on the sensitivity and specificity of the assay and may be influenced by several factors such as: assay methodology, sample handling, timing of sample collection, concomitant medication, and underlying disease. For these reasons, comparison of the incidence of antibodies to Insulin Degludec with the incidence of antibodies in other studies or to other products may be misleading.

In a 52-week trial of adult insulin-experienced type 1 diabetes patients, 68.9% of patients who received Insulin Degludec were positive at baseline for anti-insulin degludec antibodies and 12.3% of the patients developed anti-insulin degludec antibodies at least once during the trial. In a 52-week trial of pediatric insulin-experienced type 1 diabetes patients, 84.1% of patients who received Insulin Degludec were positive at baseline for anti-insulin degludec antibodies and 5.8% of patients developed anti-insulin degludec antibodies at least once during the trial. In a 52-week trial of adult insulin-naïve type 2 diabetes patients, 1.7% of patients who received Insulin Degludec were positive at baseline for anti-insulin degludec antibodies and 6.2% of patients developed anti-insulin degludec antibodies at least once during the trial. In these trials, between 96.7% and 99.7% of patients who were positive for anti-insulin degludec antibodies were also positive for anti-human insulin antibodies.

6.3 Postmarketing Experience

The following additional adverse reactions have been identified during post-approval use of Insulin Degludec. Because these reactions are reported voluntarily from a population of uncertain size, it is not always possible to reliably estimate their frequency or establish a causal relationship to drug exposure.

Localized cutaneous amyloidosis at the injection site has occurred. Hyperglycemia has been reported with repeated insulin injections into areas of localized cutaneous amyloidosis; hypoglycemia has been reported with a sudden change to an unaffected injection site.

7 DRUG INTERACTIONS

Table 5 includes clinically significant drug interactions with Insulin Degludec.

Table 5: Clinically Significant Drug Interactions with Insulin Degludec

Drugs That May Increase the Risk of Hypoglycemia
Drugs: | Antidiabetic agents, ACE inhibitors, angiotensin II receptor blocking agents, disopyramide, fibrates, fluoxetine, monoamine oxidase inhibitors, pentoxifylline, pramlintide, salicylates, somatostatin analogs (e.g., octreotide), and sulfonamide antibiotics, GLP-1 receptor agonists, DPP-4 inhibitors, SGLT-2 inhibitors.
Intervention: | Dosage reductions and increased frequency of glucose monitoring may be required when Insulin Degludec is co-administered with these drugs.
Drugs That May Decrease the Blood Glucose Lowering Effect of Insulin Degludec
Drugs: | Atypical antipsychotics (e.g., olanzapine and clozapine), corticosteroids, danazol, diuretics, estrogens, glucagon, isoniazid, niacin, oral contraceptives, phenothiazines, progestogens (e.g., in oral contraceptives), protease inhibitors, somatropin, sympathomimetic agents (e.g., albuterol, epinephrine, terbutaline), and thyroid hormones.
Intervention: | Dosage increases and increased frequency of glucose monitoring may be required when Insulin Degludec is co-administered with these drugs.
Drugs That May Increase or Decrease the Blood Glucose Lowering Effect of Insulin Degludec
Drugs: | Alcohol, beta-blockers, clonidine, and lithium salts. Pentamidine may cause hypoglycemia, which may sometimes be followed by hyperglycemia.
Intervention: | Dosage adjustment and increased frequency of glucose monitoring may be required when Insulin Degludec is co-administered with these drugs.
Drugs That May Blunt Signs and Symptoms of Hypoglycemia
Drugs: | Beta-blockers, clonidine, guanethidine, and reserpine
Intervention: | Increased frequency of glucose monitoring may be required when Insulin Degludec is co-administered with these drugs.

8 USE IN SPECIFIC POPULATIONS

8.1 Pregnancy

Risk Summary

Available data from one unpublished trial and the published literature with Insulin Degludec use during pregnancy have not identified a drug-associated risk of major birth defects, miscarriage, or other adverse maternal or fetal outcomes. In a randomized, parallel-group, open-label actively controlled clinical trial that included 91 pregnant women with type 1 diabetes who were administered Insulin Degludec once daily and insulin aspart, beginning in gestational weeks 8 to 13 or prior to conception, no clear evidence of maternal or fetal risk associated with Insulin Degludec use was observed (see Data). There are risks to the mother and fetus associated with poorly controlled diabetes in pregnancy (see Clinical Considerations).

Rats and rabbits were exposed to insulin degludec in animal reproduction studies during organogenesis. Pre-and post-implantation losses and visceral/skeletal abnormalities were observed in rats at doses 5 times (rat) and at 10 times (rabbit) the human exposure at a dose of 0.75 U/kg/day. These effects were similar to those observed in rats administered human insulin (NPH) (see Data).

In the U.S. general population, the estimated background risk of major birth defects and miscarriage in clinically recognized pregnancies is 2 to 4% and 15 to 20%, respectively. The estimated background risk of major birth defects is 6 to 10% in women with pre-gestational diabetes with a peri-conceptional HbA1c >7 and has been reported to be as high as 20 to 25% in women with a peri-conceptional HbA1c >10. The estimated background risk of miscarriage for the indicated population is unknown.

Clinical Considerations

Disease-Associated Maternal and/or Embryo/fetal Risk

Hypoglycemia and hyperglycemia occur more frequently during pregnancy in patients with pre-gestational diabetes. Poorly controlled diabetes in pregnancy increases the maternal risk for diabetic ketoacidosis, pre-eclampsia, spontaneous abortions, preterm delivery, and delivery complications. Poorly controlled diabetes increases the fetal risk for major birth defects, still birth, and macrosomia related morbidity.

Data

Human Data

In an open-label clinical trial, 185 pregnant females with type 1 diabetes were treated with either Insulin Degludec (once daily) or insulin detemir (once or twice daily); both groups received insulin aspart 2 to 4 times daily with meals. There were no significant drug-associated differences in pregnancy outcomes or the health of the fetus and newborn between the two groups. In this study, the proportion of subjects with severe hypoglycemia and hypoglycemia was similar between the two treatment arms; for the definitions of severe hypoglycemia and hypoglycemia [see Adverse Reactions (6.1)]. Poor glucose control during pregnancy in both groups and small sample size were limitations of the study.

In about two thirds of infants, insulin degludec was detected in the infant cord blood at levels above the lower level of quantification of the assay.

Animal Data

Insulin degludec was investigated in studies covering fertility, embryo-fetal development and pre- and post-natal development in rats and during the period of embryo-fetal development in rabbits. Human insulin (NPH insulin) was included as comparator. In these studies, insulin degludec caused pre- and post-implantation losses and visceral/skeletal abnormalities when given subcutaneously at up to 21 U/kg/day in rats and 3.3 U/kg/day in rabbits, resulting in 5 times (rat) and 10 times (rabbit) the human exposure (AUC) at a human subcutaneous dose of 0.75 U/kg/day. Overall, the effects of insulin degludec were similar to those observed with human insulin, which were probably secondary to maternal hypoglycemia.

8.2 Lactation

Risk Summary

There are no data on the presence of insulin degludec in human milk, the effects on the breastfed infant, or the effects on milk production. Insulin degludec is present in rat milk [see Data]. The developmental and health benefits of breastfeeding should be considered along with the mother’s clinical need for Insulin Degludec and any potential adverse effects on the breastfed infant from Insulin Degludec or from the underlying maternal condition.

Data

In lactating rats, insulin degludec was present in milk at a concentration lower than that in plasma.

8.4 Pediatric Use

The safety and effectiveness of Insulin Degludec to improve glycemic control in pediatric patients 1 year of age or older with diabetes mellitus have been established. The use of Insulin Degludec for this indication is supported by evidence from an adequate and well-controlled trial and a pharmacokinetic study (trials included pediatric patients 1 year of age and older with type 1 diabetes mellitus) [see Clinical Pharmacology (12.3) and Clinical Studies (14.2)]. The use of Insulin Degludec in pediatric patients 1 year of age and older with type 2 diabetes mellitus is also supported by evidence from adequate and well-controlled trials in adults with type 2 diabetes mellitus [see Clinical Studies (14.3)].

In pediatric patients 1 year of age and older already on insulin therapy, start Insulin Degludec at a reduced dose to minimize the risk of hypoglycemia [see Dosage and Administration (2.4)].

The safety and effectiveness of Insulin Degludec have not been established in pediatric patients less than 1-year-old.

8.5 Geriatric Use

In controlled clinical trials [see Clinical Studies (14)] a total of 77 (7%) of the 1102 Insulin Degludec-treated patients with type 1 diabetes were 65 years or older and 9 (1%) were 75 years or older. A total of 670 (25%) of the 2713 Insulin Degludec-treated patients with type 2 diabetes were 65 years or older and 80 (3%) were 75 years or older. Differences in safety or effectiveness were not suggested in subgroup analyses comparing subjects older than 65 years to younger subjects.

In the safety outcomes trial (DEVOTE), a total of 1983 (52%) of the 3818 Insulin Degludec-treated patients with type 2 diabetes were 65 years or older and 381 (10%) were 75 years or older. Differences in safety or effectiveness were not observed in these subgroup analyses.

Nevertheless, greater caution should be exercised when Insulin Degludec is administered to geriatric patients since greater sensitivity of some older individuals to the effects of Insulin Degludec cannot be ruled out. The initial dosing, dose increments, and maintenance dosage should be conservative to avoid hypoglycemia. Hypoglycemia may be more difficult to recognize in the geriatric patients.

8.6 Renal Impairment

In clinical trials [see Clinical Studies (14)] a total of 75 (7%) of the 1102 Insulin Degludec-treated patients with type 1 diabetes had an eGFR less than 60 mL/min/1.73 m^2 and 1 (0.1%) had an eGFR less than 30 mL/min/1.73 m^2. A total of 250 (9%) of the 2713 Insulin Degludec-treated patients with type 2 diabetes had an eGFR less than 60 mL/min/1.73 m^2 and no subjects had an eGFR less than 30 mL/min/1.73 m^2.

In the safety outcomes trial (DEVOTE), a total of 1429 (37.4%) of the 3818 Insulin Degludec-treated patients with type 2 diabetes had an eGFR less than 60 mL/min/1.73 m^2, and 108 (2.8%) subjects had an eGFR less than 30 mL/min/1.73 m^2. Differences in safety or effectiveness were not observed in the subgroup analyses.

No clinically relevant difference in the pharmacokinetics of Insulin Degludec was identified in a study comparing healthy subjects and subjects with kidney impairment including subjects with end stage kidney disease [see Clinical Pharmacology (12.3)]. However, as with all insulin products, glucose monitoring should be intensified and the Insulin Degludec dosage adjusted on an individual basis in patients with kidney impairment.

8.7 Hepatic Impairment

No difference in the pharmacokinetics of Insulin Degludec was identified in a study comparing healthy subjects and subjects with hepatic impairment (mild, moderate, and severe hepatic impairment) [see Clinical Pharmacology (12.3)]. However, as with all insulin products, glucose monitoring should be intensified and the Insulin Degludec dosage adjusted on an individual basis in patients with hepatic impairment.

10 OVERDOSAGE

An excess of insulin relative to food intake, energy expenditure, or both may lead to severe and sometimes prolonged and life-threatening hypoglycemia and hypokalemia [see Warnings and Precautions (5.3, 5.6)]. Mild episodes of hypoglycemia usually can be treated with oral glucose. Lowering the insulin dosage, and adjustments in meal patterns or exercise may be needed. More severe episodes of hypoglycemia with coma, seizure, or neurologic impairment may be treated with a glucagon for emergency use or concentrated intravenous glucose. After apparent clinical recovery from hypoglycemia, continued observation and additional carbohydrate intake may be necessary to avoid reoccurrence of hypoglycemia. Hypokalemia must be corrected appropriately.

11 DESCRIPTION

Insulin degludec is a long-acting basal human insulin analog for subcutaneous injection produced by a process that includes expression of recombinant DNA in Saccharomyces cerevisiae followed by chemical modification.

Insulin degludec differs from human insulin in that the amino acid threonine in position B30 has been omitted and a side-chain consisting of glutamic acid and a C16 fatty acid has been attached (chemical name: LysB29(Nε-hexadecandioyl-γ-Glu) des(B30) human insulin). Insulin degludec has a molecular formula of C274H411N65O81S6 and a molecular weight of 6.104 kDa. It has the following structure:

Figure 1: Structural Formula of Insulin Degludec

Insulin Degludec injection is a sterile, aqueous, clear, and colorless solution available as 100 units/mL (U-100) or 200 units/mL (U-200) for subcutaneous use.

For the 100 units/mL solution, each mL contains 100 units of insulin degludec and glycerin (19.6 mg), metacresol (1.72 mg), phenol (1.5 mg), zinc (32.7 mcg), and Water for Injection, USP.

For the 200 units/mL solution, each mL contains 200 units of insulin degludec and glycerin (19.6 mg), metacresol (1.72 mg), phenol (1.5 mg), zinc (71.9 mcg), and Water for Injection, USP.

Insulin Degludec has a pH of approximately 7.6. Hydrochloric acid or sodium hydroxide may be added to adjust pH.

12 CLINICAL PHARMACOLOGY

12.1 Mechanism of Action

The primary activity of insulin, including Insulin Degludec, is regulation of glucose metabolism. Insulin and its analogs lower blood glucose by stimulating peripheral glucose uptake, especially by skeletal muscle and fat, and by inhibiting hepatic glucose production. Insulin also inhibits lipolysis and proteolysis, and enhances protein synthesis. Insulin Degludec forms multi-hexamers when injected into the subcutaneous tissue resulting in a subcutaneous insulin degludec depot. The protracted time action profile of Insulin Degludec is predominantly due to delayed absorption of insulin degludec from the subcutaneous tissue to the systemic circulation and to a lesser extent due to binding of insulin-degludec to circulating albumin.

12.2 Pharmacodynamics

The glucose-lowering effect of Insulin Degludec after 8 days of once-daily dosing was measured in a euglycemic glucose clamp study enrolling 21 patients with type 1 diabetes. Figure 2 shows the pharmacodynamic effect of Insulin Degludec over time following 8 once-daily subcutaneous injections of 0.4 U/kg of Insulin Degludec in patients with type 1 diabetes.

Figure 2: Mean GIR Profile for 0.4 units/kg Dose of Insulin Degludec (Steady State) in Patients with Type 1 Diabetes Mellitus

The mean maximum glucose lowering effect (GIRmax) of a 0.4 units/kg dose of Insulin Degludec was 2.0 mg/kg/min, which was observed at a median of 12 hours post-dose. The glucose lowering effect of Insulin Degludec lasted at least 42 hours after the last of 8 once-daily injections.

In patients with type 1 diabetes mellitus, the steady-state, within subjects, day-to-day variability in total glucose lowering effect was 20% with Insulin Degludec (within-subject coefficient of variation for AUCGIR,τ,SS).

The total glucose-lowering effect of Insulin Degludec over 24 hours measured in a euglycemic clamp study after 8 days of once-daily administration in patients with type 1 diabetes increases approximately in proportion to the dose for doses between 0.4 units/kg to 0.8 units/kg.

The total glucose-lowering effect of 0.4 units/kg of Insulin Degludec U-100 and 0.4 units/kg of Insulin Degludec U-200, administered at the same dose, and assessed over 24 hours in a euglycemic clamp study after 8 days of once-daily injection was comparable.

12.3 Pharmacokinetics

Absorption

In patients with type 1 diabetes, after 8 days of once daily subcutaneous dosing with 0.4 units/kg of Insulin Degludec, maximum degludec concentrations of 4472 pmol/L were attained at a median of 9 hours (tmax). After the first dose of Insulin Degludec, median onset of appearance was around one hour.

Total insulin degludec concentration (i.e., exposure) increased in a dose proportional manner after subcutaneous administration of 0.4 units/kg to 0.8 units/kg Insulin Degludec. Total and maximum insulin degludec exposure at steady state are comparable between Insulin Degludec U-100 and Insulin Degludec U-200 when each is administered at the same units/kg dose.

Insulin degludec concentration reached steady state levels after 3-4 days of Insulin Degludec administration [see Dosage and Administration (2.2)].

Distribution

The affinity of insulin degludec to serum albumin corresponds to a plasma protein binding of >99% in human plasma. The results of the in vitro protein binding studies demonstrate that there is no clinically relevant interaction between insulin degludec and other protein bound drugs.

Elimination

The half-life after subcutaneous administration is determined primarily by the rate of absorption from the subcutaneous tissue. On average, the half-life at steady state is approximately 25 hours independent of dose. Degradation of Insulin Degludec is similar to that of insulin human; all metabolites formed are inactive. The mean apparent clearance of insulin degludec is 0.03 L/kg (2.1 L/h in 70 kg patient) after single subcutaneous dose of 0.4 units/kg.

Specific Populations

Pediatrics-

Population pharmacokinetic analysis was conducted for Insulin Degludec using data from 199 pediatric subjects (1 to <18 years of age) with type 1 diabetes. Body weight was a significant covariate affecting the clearance of Insulin Degludec. After adjusting for body weight, the total exposure of Insulin Degludec at steady state was independent of age.

Geriatrics-

Pharmacokinetic and pharmacodynamic response of Insulin Degludec was compared in 13 younger adult (18−35 years) and 14 geriatric (≥65 years) subjects with type 1 diabetes following two 6-day periods of once-daily subcutaneous dosing with 0.4 units/kg dose of Insulin Degludec or insulin glargine. On average, the pharmacokinetic and pharmacodynamic properties of Insulin Degludec at steady-state were similar in younger adult and geriatric subjects, albeit with greater between subject variability among the geriatric subjects.

Gender-

The effect of gender on the pharmacokinetics of Insulin Degludec was examined in an across-trial analysis of the pharmacokinetic and pharmacodynamic studies conducted using unit/kg doses of Insulin Degludec. Overall, there were no clinically relevant differences in the pharmacokinetic properties of insulin degludec between female and male subjects.

Obesity-

The effect of BMI on the pharmacokinetics of Insulin Degludec was explored in a cross-trial analysis of pharmacokinetic and pharmacodynamic studies conducted using unit/kg doses of Insulin Degludec. For subjects with type 1 diabetes, no relationship between exposure of Insulin Degludec and BMI was observed. For subjects with type 1 and type 2 diabetes a trend for decrease in glucose-lowering effect of Insulin Degludec with increasing BMI was observed.

Race and Ethnicity-

Insulin Degludec has been studied in a pharmacokinetic and pharmacodynamic study in Black or African American subjects not of Hispanic or Latino origin (N=18), White subjects of Hispanic or Latino origin (N=22) and White subjects not of Hispanic or Latino origin (N=23) with type 2 diabetes mellitus conducted using unit/kg doses of Insulin Degludec. There were no statistically significant differences in the pharmacokinetic and pharmacodynamic properties of Insulin Degludec between the racial and ethnic groups investigated.

Pregnancy-

The effect of pregnancy on the pharmacokinetics and pharmacodynamics of Insulin Degludec has not been studied [see Use in Specific Populations (8.1)].

Renal Impairment-

Insulin Degludec pharmacokinetics was studied in 32 subjects (N=4-8/group) with normal or impaired renal function/end-stage renal disease following administration of a single subcutaneous dose (0.4 units/kg) of Insulin Degludec. Renal function was defined using creatinine clearance (Clcr) as follows: ≥90 mL/min (normal), 60-89 mL/min (mild), 30-59 mL/min (moderate) and <30 mL/min (severe). Subjects requiring dialysis were classified as having end-stage renal disease (ESRD). Total (AUCIDeg,0-120h,SD) and peak exposure of Insulin Degludec were on average about 10-25% and 13-27% higher, respectively in subjects with mild to severe renal impairment except subjects with ESRD who showed similar exposure as compared to subjects with normal renal function. No systematic trend was noted for this increase in exposure across different renal impairment subgroups. Hemodialysis did not affect clearance of Insulin Degludec (CL/FIDeg,SD) in subjects with ESRD [see Use in Specific Populations (8.6)].

Hepatic Impairment-

Insulin Degludec has been studied in a pharmacokinetic study in 24 subjects (N=6/group) with normal or impaired hepatic function (mild, moderate, and severe hepatic impairment) following administration of a single subcutaneous dose (0.4 units/kg) of Insulin Degludec. Hepatic function was defined using Child-Pugh Scores ranging from 5 (mild hepatic impairment) to 15 (severe hepatic impairment). No differences in the pharmacokinetics of Insulin Degludec were identified between healthy subjects and subjects with hepatic impairment [see Use in Specific Populations (8.7)].

13 NONCLINICAL TOXICOLOGY

13.1 Carcinogenesis, Mutagenesis, Impairment of Fertility

Standard 2-year carcinogenicity studies in animals have not been performed to evaluate the carcinogenic potential of insulin degludec. In a 52-week study including human insulin (NPH insulin) as comparator (6.7 units/kg/day), Sprague-Dawley rats were dosed subcutaneously with insulin degludec at 3.3, 6.7, and 10 units/kg/day, resulting in 5 times the human exposure (AUC) when compared to a human subcutaneous dosage of 0.75 units/kg/day. Human insulin was dosed at 6.7 units/kg/day. No treatment-related increases in incidences of hyperplasia, benign or malignant tumors were recorded in female mammary glands from rats dosed with insulin degludec and no treatment related changes in the female mammary gland cell proliferation were found using BrdU incorporation. Further, no treatment related changes in the occurrence of hyperplastic or neoplastic lesions were seen in other tissues in animals dosed with insulin degludec when compared to vehicle or human insulin.

Genotoxicity testing of insulin degludec was not performed.

In a combined fertility and embryo-fetal study in male and female rats, treatment with insulin degludec up to 21 units/kg/day (approximately 5 times the human subcutaneous dose of 0.75 units/kg/day, based on units/body surface area) prior to mating and in female rats during gestation had no effect on mating performance and fertility.

14 CLINICAL STUDIES

The efficacy of Insulin Degludec administered once-daily either at the same time each day or at any time each day in patients with type 1 diabetes and used in combination with a mealtime insulin was evaluated in three randomized, open-label, treat-to-target, active-controlled trials in adults and one randomized, open-label, treat-to-target, active-controlled trial in pediatric patients 1 year of age and older. The efficacy of Insulin Degludec administered once-daily either at the same time each day or at any time each day in adult patients with type 2 diabetes and used in combination with a mealtime insulin or in combination with common oral anti-diabetic agents was evaluated in six randomized, open-label, treat-to-target active-controlled trials.

Adult patients treated with Insulin Degludec achieved levels of glycemic control similar to those achieved with LANTUS (insulin glargine 100 units/mL) and LEVEMIR (insulin detemir) and achieved statistically significant improvements compared to sitagliptin.

14.1 Type 1 Diabetes – Adult

Insulin Degludec Administered at the Same Time Each Day in Combination with a Rapid-Acting Insulin Analog at Mealtimes in Adult Patients

Study A

The efficacy of Insulin Degludec was evaluated in a 52-week randomized, open-label, multicenter trial in 629 patients with type 1 diabetes mellitus (Study A). Patients were randomized to Insulin Degludec once-daily with the evening meal or insulin glargine U-100 once-daily according to the approved labeling. Insulin aspart was administered before each meal in both treatment arms.

The mean age of the trial population was 43 years and mean duration of diabetes was 19 years. 59% were male. 93% were White, 2% Black or African American. 5% were Hispanic. 9% of patients had eGFR<60 mL/min/1.73m^2. The mean BMI was approximately 26.3 kg/m^2.

At week 52, the difference in HbA1c reduction from baseline between Insulin Degludec and insulin glargine U-100 was -0.01% with a 95% confidence interval of [-0.14%; 0.11%] and met the pre-specified non-inferiority margin (0.4%). See Table 6, Study A.

Study B

The efficacy of Insulin Degludec was evaluated in a 26-week randomized, open-label, multicenter trial in 455 patients with type 1 diabetes mellitus (Study B). Patients were randomized to Insulin Degludec or insulin detemir once-daily in the evening. After 8 weeks, insulin detemir could be dosed twice-daily. 67% used insulin detemir once daily at end of trial. 33% used insulin detemir twice daily at end of trial. Insulin aspart was administered before each meal in both treatment arms.

The mean age of the trial population was 41 years and mean duration of diabetes was 14 years. 52% were male. 45% were White, 0.4% Black or African American. 4% were Hispanic. 4% of patients had eGFR<60 mL/min/1.73m^2. The mean BMI was approximately 23.9 kg/m^2.

At week 26, the difference in HbA1c reduction from baseline between Insulin Degludec and insulin detemir was -0.09% with a 95% confidence interval of [-0.23%; 0.05%] and met the pre-specified non-inferiority margin (0.4%). See Table 6, Study B.

Table 6: Results at Week 52 in a Trial Comparing Insulin Degludec to Insulin Glargine U-100 (Study A) and Week 26 in a Trial Comparing Insulin Degludec to Insulin Detemir (Study B) in Adult Patients with Type 1 Diabetes Mellitus Receiving Insulin Aspart at Mealtimes

 | Study A |  | Study B
 | Insulin Degludec + Insulin aspart | Insulin glargine U-100 + Insulin aspart | Insulin Degludec + Insulin aspart | Insulin detemir + Insulin aspart
N | 472 | 157 | 302 | 153
HbA1c (%)
Baseline | 7.7 | 7.7 | 8.0 | 8.0
End of trial | 7.3 | 7.3 | 7.3 | 7.3
Adjusted mean change from baseline* | -0.36 | -0.34 | -0.71 | -0.61
Estimated treatment difference [95%CI]; Insulin Degludec - basal insulin U-100 | -0.01 [-0.14;0.11] |  | -0.09 [-0.23;0.05]
Proportion Achieving HbA1c < 7% at Trial End | 39.8% | 42.7% | 41.1% | 37.3%
FPG (mg/dL)
Baseline | 165 | 174 | 178 | 171
End of trial | 141 | 149 | 131 | 161
Adjusted mean change from baseline | -27.6 | -21.6 | -43.3 | -13.5
Daily basal insulin dose
Baseline mean | 28 U | 26 U | 22 U | 22 U
Mean dose at end of study | 29 U^1 | 31 U^1 | 25 U^2 | 29 U^2
Daily bolus insulin dose
Baseline mean | 29 U | 29 U | 28 U | 31 U
Mean dose at end of study | 32 U^1 | 35 U^1 | 36 U^2 | 41 U^2

^1At Week 52
^2At Week 26
*The change from baseline to end of treatment visit in HbA1c was analyzed using ANOVA with treatment, region, sex, and anti-diabetic treatment at screening as fixed effects, and age and baseline HbA1c as covariates.
In Study A, there were 14.8% of subjects in the Insulin Degludec and 11.5% Insulin glargine arms for whom data was missing at the time of the HbA1c measurement.
In Study B, there were 6.3% of subjects in the Insulin Degludec and 9.8% Insulin detemir arms for whom data was missing at the time of the HbA1c measurement.

Study C: Insulin Degludec Administered at the Same Time Each Day or at Any Time Each Day in Combination with a Rapid-Acting Insulin Analog at Mealtimes in Adult Patients

The efficacy of Insulin Degludec was evaluated in a 26-week randomized, open-label, multicenter trial in 493 patients with type 1 diabetes mellitus. Patients were randomized to Insulin Degludec injected once-daily at the same time each day (with the main evening meal), to Insulin Degludec injected once daily at any time each day or to insulin glargine U-100 injected once-daily according to the approved labeling. The any time each day Insulin Degludec arm was designed to simulate a worst-case scenario injection schedule of alternating short and long, once daily, dosing intervals (i.e., alternating intervals of 8 to 40 hours between doses). Insulin Degludec in this arm was dosed in the morning on Monday, Wednesday, and Friday and in the evening on Tuesday, Thursday, Saturday, and Sunday. Insulin aspart was administered before each meal in all treatment arms.

The mean age of the trial population was 44 years and mean duration of diabetes was 19 years. 58% were male. 98% were White, 2% Black or African American. 3% were Hispanic. 7% of patients had eGFR<60 mL/min/1.73m^2. The mean BMI was approximately 26.7 kg/m^2.

At week 26, the difference in HbA1c reduction from baseline between Insulin Degludec administered at alternating times and insulin glargine U-100 was 0.17% with a 95% confidence interval of [0.04%; 0.30%] and met the pre-specified non-inferiority margin (0.4%). See Table 7.

Table 7: Results at Week 26 in a Trial Comparing Insulin Degludec Dosed Once Daily at the Same and at Alternating Times Each Day to Insulin Glargine U-100 in Adult Patients with Type 1 Diabetes Mellitus Receiving Insulin Aspart at Mealtimes

 | Insulin Degludec at the same time each day + Insulin aspart | Insulin Degludec at alternating times + Insulin aspart | Insulin glargine U-100 + Insulin aspart
N | 165 | 164 | 164
HbA1c (%)
Baseline | 7.7 | 7.7 | 7.7
End of trial | 7.3 | 7.3 | 7.1
Adjusted mean change from baseline* | -0.41 | -0.40 | -0.57
Estimated treatment difference [95%CI]; Insulin Degludec alternating - Insulin glargine U-100 |  | 0.17 [0.04;0.30]
Proportion Achieving HbA1c < 7% at Trial End | 37.0% | 37.2% | 40.9%
FPG (mg/dL)
Baseline | 179 | 173 | 175
End of trial | 133 | 149 | 151
Adjusted mean change from baseline | -41.8 | -24.7 | -23.9
Daily basal insulin dose
Baseline mean | 28 U | 29 U | 29 U
Mean dose at end of study | 32 U | 36 U | 35 U
Daily bolus insulin dose
Baseline mean | 29 U | 33 U | 32 U
Mean dose at end of study | 27 U | 30 U | 35 U

*The change from baseline to end of treatment visit in HbA1c was analyzed using ANOVA with treatment, region, sex, and anti-diabetic treatment at screening as fixed effects, and age and baseline HbA1c as covariates.

In Study C, there were 15.8% and 15.9% of subjects in the Insulin Degludec (same time and alternating times respectively) and 7.9% Insulin glargine arms for whom data was missing at the time of the HbA1c measurement.

14.2 Type 1 Diabetes – Pediatric Patients 1 Year of Age and Older

Study J: Insulin Degludec Administered at the Same Time Each Day in Combination with a Rapid-Acting Insulin Analog at Mealtimes in Pediatric Patients 1 Year of Age and Older

The efficacy of Insulin Degludec was evaluated in a 26-week, randomized, open label, multicenter trial in 350 patients with type 1 diabetes mellitus (Study J). Patients were randomized to Insulin Degludec once-daily or insulin detemir once or twice-daily. Subjects on a twice-daily insulin detemir regimen were dosed at breakfast and in the evening either with the main evening meal or at bedtime. Insulin aspart was administered before each main meal in both treatment arms. At end of trial, 36% used insulin detemir once daily and 64% used insulin detemir twice daily.

The mean age of the trial population was 10 years; 24% were ages 1-5 years; 39% were ages 6-11 years and 36% were ages 12-17 years. The mean duration of diabetes was 4 years. 55% were male. 75% were White, 3% Black or African American. 3% were Hispanic. The mean z-score for body weight was 0.31.

At week 26, the difference in HbA1c reduction from baseline between Insulin Degludec and insulin detemir was 0.15% with a 95% confidence interval of [-0.03%; 0.33%] and met the pre-specified non-inferiority margin (0.4%). See Table 8.

Table 8: Results at Week 26 in a Trial Comparing Insulin Degludec to Insulin Detemir in Pediatric Patients 1 Year of Age and Older with Type 1 Diabetes Mellitus Receiving Insulin Aspart at Mealtimes

 | Insulin Degludec + Insulin aspart | Insulin detemir + Insulin aspart
N | 174 | 176
HbA1c (%)
Baseline | 8.2 | 8.0
End of 26 weeks | 8.0 | 7.7
Adjusted mean change from baseline after 26 weeks ± | -0.19 | -0.34
Estimated treatment difference [95%CI]; Insulin Degludec v. Insulin detemir | 0.15 [ -0.03; 0.33]
FPG (mg/dL)
Baseline | 162 | 151
End of 26 weeks | 150 | 160
Adjusted mean change from baseline after 26 weeks | 52.0 | 59.6
Daily basal insulin dose
Baseline mean | 15 U (0.37 U/kg) | 16 U (0.41 U/kg)
Mean dose after 26 weeks | 16 U (0.37 U/kg) | 22 U (0.51 U/kg)
Daily bolus insulin dose
Baseline mean | 20 U (0.50 U/kg) | 20 U (0.52 U/kg)
Mean dose after 26 weeks | 23 U (0.56 U/kg) | 22 U (0.57 U/kg)

±The change from baseline to end of treatment visit in HbA1c was analyzed using ANOVA with missing data imputed by multiple imputation carrying forward the baseline value and adding the error term, with treatment, region, sex, and age group as fixed factors, and baseline HbA1c as covariate.
In Study J, there were 2.9% of subjects in Insulin Degludec and 6.3% Insulin detemir arms for whom data was missing at the 26-week HbA1c measurement.

14.3 Type 2 Diabetes - Adult

Study D: Insulin Degludec Administered at the Same Time Each Day as an Add-on to Metformin with or without a DPP-4 Inhibitor in Insulin Naïve Adult Patients

The efficacy of Insulin Degludec was evaluated in a 52-week randomized, open-label, multicenter trial that enrolled 1030 insulin naïve patients with type 2 diabetes mellitus inadequately controlled on one or more oral antidiabetic agents (OADs). Patients were randomized to Insulin Degludec once-daily with the evening meal or insulin glargine U-100 once-daily according to the approved labeling. Metformin alone (83%) or in combination with a DPP-4 inhibitor (18%) was used as background therapy in both treatment arms.

The mean age of the trial population was 59 years and mean duration of diabetes was 9 years. 62% were male. 88% were White, 7% Black or African American. 17% were Hispanic. 10% of patients had eGFR<60 mL/min/1.73m^2. The mean BMI was approximately 31.1 kg/m^2.

At week 52, the difference in HbA1c reduction from baseline between Insulin Degludec and insulin glargine U-100 was 0.09% with a 95% confidence interval of [-0.04%; 0.22%] and met the pre-specified non-inferiority margin (0.4%); See Table 9.

Table 9: Results at Week 52 in a Trial Comparing Insulin Degludec to Insulin Glargine U-100 in Adult Patients with Type 2 Diabetes Mellitus on OAD(s)*

 | Insulin Degludec; + OAD(s)* |  | Insulin glargine U-100 + OAD(s)*
N | 773 |  | 257
HbA1c (%)
Baseline | 8.2 |  | 8.2
End of trial | 7.1 |  | 7.0
Adjusted mean change from baseline** | -1.06 |  | -1.15
Estimated treatment difference [95%CI]; Insulin Degludec - Insulin glargine U-100 | 0.09 [-0.04;0.22]
Proportion Achieving HbA1c < 7% at Trial End | 51.7% | 54.1%
FPG (mg/dL)
Baseline | 174 |  | 174
End of trial | 106 |  | 115
Adjusted mean change from baseline | -68.0 |  | -60.2
Daily insulin dose
Baseline mean (starting dose) | 10 U |  | 10 U
Mean dose after 52 weeks | 56 U |  | 58 U

*OAD: oral antidiabetic agent
**The change from baseline to end of treatment visit in HbA1c was analyzed using ANOVA with treatment, region, sex, and anti-diabetic treatment at screening as fixed effects, and age and baseline HbA1c as covariates.
In Study D, there were 20.6% of subjects in the Insulin Degludec and 22.2% Insulin glargine arms for whom data was missing at the time of the HbA1c measurement.

Study E: Insulin Degludec U-200 Administered at the Same Time Each Day as an Add-on to Metformin with or without a DPP-4 Inhibitor in Insulin Naïve Adult Patients

The efficacy of Insulin Degludec U-200 was evaluated in a 26-week randomized, open-label, multicenter trial in 457 insulin naïve patients with type 2 diabetes mellitus inadequately controlled on one or more oral antidiabetic agents (OADs) at baseline. Patients were randomized to Insulin Degludec U-200 once-daily with the evening meal or insulin glargine U-100 once-daily according to the approved labeling. Both treatment arms were receiving metformin alone (84%) or in combination with a DPP-4 inhibitor (16%) as background therapy.

The mean age of the trial population was 58 years and mean duration of diabetes was 8 years. 53% were male. 78% were White, 14% Black or African American. 8% were Hispanic. 8% of patients had eGFR <60 mL/min/1.73m^2. The mean BMI was approximately 32.4 kg/m^2.

At week 26, the difference in HbA1c reduction from baseline between Insulin Degludec U-200 and insulin glargine U-100 was 0.04% with a 95% confidence interval of [-0.11%; 0.19%] and met the pre-specified non-inferiority margin (0.4%). See Table 10.

Table 10: Results at Week 26 in a Trial Comparing Insulin Degludec U-200 to Insulin Glargine U-100 in Adult Patients with Type 2 Diabetes Mellitus on OAD(s)*

 | Insulin Degludec U-200 + Met ± DPP-4 |  | Insulin glargine U-100 + Met ± DPP-4
N | 228 |  | 229
HbA1c (%)
Baseline | 8.3 |  | 8.2
End of trial | 7.0 |  | 6.9
Adjusted mean change from baseline** | -1.18 |  | -1.22
Estimated treatment difference [95%CI]; Insulin Degludec - Insulin glargine U-100 | 0.04 [-0.11;0.19]
Proportion Achieving HbA1c < 7% at Trial End | 52.2% | 55.9%
FPG (mg/dL)
Baseline | 172 |  | 174
End of trial | 106 |  | 113
Adjusted mean change from baseline | -71.1 |  | -63.5
Daily insulin dose
Baseline mean | 10 U |  | 10 U
Mean dose after 26 weeks | 59 U |  | 62 U

*OAD: oral antidiabetic agent
**The change from baseline to end of treatment visit in HbA1c was analyzed using ANOVA with treatment, region, sex, and anti-diabetic treatment at screening as fixed effects, and age and baseline HbA1c as covariates.
In Study E, there were 12.3% of subjects in the Insulin Degludec and 12.7% Insulin glargine arms for whom data was missing at the time of the HbA1c measurement.

Study F: Insulin Degludec Administered at the Same Time Each Day in Insulin Naïve Adult Patients as an Add-on to One or More of the Following Oral Agents: Metformin, Sulfonylurea, Glinides or Alpha-Glucosidase Inhibitors

The efficacy of Insulin Degludec was evaluated in a 26-week randomized, open-label, multicenter trial in Asia in 435 insulin naïve patients with type 2 diabetes mellitus inadequately controlled on one or more oral antidiabetic agents (OADs) at baseline. Patients were randomized to Insulin Degludec once-daily in the evening or insulin glargine U-100 once-daily according to the approved labeling. Pre-trial oral antidiabetes agents were continued as background therapy except for DPP-4 inhibitors or thiazolidinediones in both treatment arms.

The mean age of the trial population was 59 years and mean duration of diabetes was 12 years. 54% were male. All patients were Asian. 11% of patients had eGFR<60 mL/min/1.73m^2. The mean BMI was approximately 25.0 kg/m^2.

At week 26, the difference in HbA1c reduction from baseline between Insulin Degludec and insulin glargine U-100 was 0.11% with a 95% confidence interval of [-0.03%; 0.24%] and met the pre-specified non-inferiority margin (0.4%). See Table 11.

Table 11: Results at Week 26 in a Trial Comparing Insulin Degludec to Insulin Glargine U-100 in Adult Patients with Type 2 Diabetes Mellitus on OAD(s)*

 | Insulin Degludec + OAD(s)* | Insulin glargine U-100 + OAD(s)*
N | 289 | 146
HbA1c (%)
Baseline | 8.4 | 8.5
End of trial | 7.2 | 7.1
Adjusted mean change from baseline** | -1.42 | -1.52
Estimated treatment difference [95%CI] Insulin Degludec - Insulin glargine U-100 | 0.11 [-0.03 ; 0.24]
Proportion Achieving HbA1c < 7% at Trial End | 40.8% | 48.6%
FPG (mg/dL)
Baseline | 152 | 156
End of trial | 100 | 102
Adjusted mean change from baseline | -54.6 | -53.0
Daily insulin dose
Baseline mean (starting dose) | 9 U | 9 U
Mean dose after 26 weeks | 19 U | 24 U

*OAD: oral antidiabetic agent
**The change from baseline to end of treatment visit in HbA1c was analyzed using ANOVA with treatment, region, sex, and anti-diabetic treatment at screening as fixed effects, and age and baseline HbA1c as covariates.
In Study F, there were 10% of subjects in the Insulin Degludec and 6.8% Insulin glargine arms for whom data was missing at the time of the HbA1c measurement.

Study G: Insulin Degludec Administered at the Same Time Each Day or Any Time Each Day as an Add-on to One and up to Three of the Following Oral Agents: Metformin, Sulfonylurea or Glinides or Pioglitazone in Adult Patients

The efficacy of Insulin Degludec was evaluated in a 26-week randomized, open-label, multicenter trial in 687 patients with type 2 diabetes mellitus inadequately controlled on basal insulin alone, oral antidiabetic agents (OADs) alone or both basal insulin and OAD. Patients were randomized to Insulin Degludec injected once-daily at the same time each day (with the main evening meal), to Insulin Degludec injected once daily at any time each day or to insulin glargine U-100 injected once-daily according to the approved labeling. The any time each day Insulin Degludec arm was designed to simulate a worst-case scenario injection schedule of alternating short and long, once daily, dosing intervals (i.e., alternating intervals of 8 to 40 hours between doses). Insulin Degludec in this arm was dosed in the morning on Monday, Wednesday, and Friday and in the evening on Tuesday, Thursday, Saturday, and Sunday. Up to three of the following oral antidiabetes agents (metformin, sulfonylureas, glinides or thiazolidinediones) were administered as background therapy in both treatment arms.

The mean age of the trial population was 56 years and mean duration of diabetes was 11 years. 54% were male. 67% were White, 3% Black or African American. 11% were Hispanic. 6% of patients had eGFR<60 mL/min/1.73m^2. The mean BMI was approximately 29.6 kg/m^2.

At week 26, the difference in HbA1c reduction from baseline between Insulin Degludec at alternating times and insulin glargine U-100 was 0.04% with a 95% confidence interval of [-0.12%; 0.20%]. This comparison met the pre-specified non-inferiority margin (0.4%). See Table 12.

Table 12: Results at Week 26 in a Trial Comparing Insulin Degludec at Same and Alternating Times to Insulin Glargine U-100 in Adult Patients with Type 2 Diabetes Mellitus on OAD(s)*

 | Insulin Degludec at the same time each day ± OAD(s)* | Insulin Degludec at alternating times ± OAD(s)* | Insulin glargine U-100 ± OAD(s)*
N | 228 | 229 | 230
HbA1c (%)
Baseline | 8.4 | 8.5 | 8.4
End of trial | 7.3 | 7.2 | 7.1
Adjusted mean change from baseline** | -1.03 | -1.17 | -1.21
Estimated treatment difference [95%CI]; Insulin Degludec alternating- Insulin glargine U-100 |  | 0.04 [-0.12;0.20]
Estimated treatment difference Insulin Degludec alternating –Insulin Degludec same | -0.13
Proportion Achieving HbA1c < 7% at Trial End | 40.8% | 38.9% | 43.9%
FPG (mg/dL)
Baseline | 158 | 162 | 163
End of trial | 105 | 105 | 112
Adjusted mean change from baseline | -54.2 | -55.0 | -47.5
Daily insulin dose
Baseline mean | 21 U | 19 U | 19 U
Mean dose after 26 weeks | 45 U | 46 U | 44 U

*OAD: oral antidiabetic agent
**The change from baseline to end of treatment visit in HbA1c was analyzed using ANOVA with treatment, region, sex, and anti-diabetic treatment at screening as fixed effects, and age and baseline HbA1c as covariates.
In Study G, there were 11.4% subjects for Insulin Degludec (both same time and alternating times) and 11.7% Insulin glargine arms for whom data was missing at the time of the HbA1c measurement.

Study H: Insulin Degludec Administered at the Same Time Each Day in Combination with a Rapid-Acting Insulin Analog at Mealtimes in Adult Patients

The efficacy of Insulin Degludec was evaluated in a 52-week randomized, open-label, multicenter trial in 992 patients with type 2 diabetes mellitus inadequately controlled on premix insulin, bolus insulin alone, basal insulin alone, oral antidiabetic agents (OADs) alone or any combination thereof. Patients were randomized to Insulin Degludec once-daily with the main evening meal or insulin glargine U-100 once-daily according to the approved labeling. Insulin aspart was administered before each meal in both treatment arms. Up to two of the following oral antidiabetes agents (metformin or pioglitazone) were used as background therapy in both treatment arms.

The mean age of the trial population was 59 years and mean duration of diabetes was 14 years. 54% were male. 83% were White, 10% Black or African American. 12% were Hispanic. 12% of patients had eGFR<60 mL/min/1.73m^2. The mean BMI was approximately 32.2 kg/m^2.

At week 52, the difference in HbA1c reduction from baseline between Insulin Degludec and insulin glargine U-100 was 0.08% with a 95% confidence interval of [-0.05%; 0.21%] and met the pre-specified non-inferiority margin (0.4%). See Table 13.

Table 13: Results at Week 52 in a Trial Comparing Insulin Degludec to Insulin Glargine U-100 in Adult Patients with Type 2 Diabetes Mellitus Receiving Insulin Aspart at Mealtimes and OADs*

 | Insulin Degludec + Insulin aspart ± OAD(s)* | Insulin glargine U-100 + Insulin aspart ± OAD(s)*
N | 744 | 248
HbA1c (%)
Baseline | 8.3 | 8.4
End of trial | 7.1 | 7.1
Adjusted mean change from baseline** | -1.10 | -1.18
Estimated treatment difference [95%CI]; Insulin Degludec - Insulin glargine U-100 | 0.08 [-0.05;0.21]
Proportion Achieving HbA1c < 7% at Trial End | 49.5% | 50.0%
FPG (mg/dL)
Baseline | 166 | 166
End of trial | 122 | 127
Adjusted mean change from baseline | -40.6 | -35.3
Daily basal insulin dose
Baseline mean | 42 U | 41 U
Mean dose after 52 weeks | 74 U | 67 U
Daily bolus insulin dose
Baseline mean | 33 U | 33 U
Mean dose after 52 weeks | 70 U | 73 U

*OAD: oral antidiabetic agent
**The change from baseline to end of treatment visit in HbA1c was analyzed using ANOVA with treatment, region, sex, and anti-diabetic treatment at screening as fixed effects, and age and baseline HbA1c as covariates.
In Study H, there were 16.1% of subjects in the Insulin Degludec and 14.5% Insulin glargine arms for whom data was missing at the time of the HbA1c measurement.

Study I: Insulin Degludec Administered at Any Time Each Day as an Add-on to One or Two of the Following Oral Agents: Metformin, Sulfonylurea, or Pioglitazone in Adult Patients

The efficacy of Insulin Degludec was evaluated in a 26-week randomized, open-label, multicenter trial in 447 patients with type 2 diabetes mellitus inadequately controlled on one or more oral antidiabetic agent (OADs) at baseline. Patients were randomized to Insulin Degludec once-daily at any time of day or sitagliptin once-daily according to the approved labeling. One or two of the following oral antidiabetes agents (metformin, sulfonylurea or pioglitazone) were also administered in both treatment arms.

The mean age of the trial population was 56 years and mean duration of diabetes was 8 years. 59% were male. 61% were White, 8% Black or African American. 21% were Hispanic. 6% of patients had eGFR<60 mL/min/1.73m^2. The mean BMI was approximately 30.4 kg/m^2.

At the end of 26 weeks, Insulin Degludec provided greater reduction in mean HbA1c compared to sitagliptin (p < 0.001). See Table 14.

Table 14: Results at Week 26 in a Trial Comparing Insulin Degludec to Sitagliptin in Adult Patients with Type 2 Diabetes Mellitus on OADs*

 | Insulin Degludec + OAD(s)* | Sitagliptin + OAD(s)*
N | 225 | 222
HbA1c (%)
Baseline | 8.8 | 9.0
End of trial | 7.2 | 7.7
Adjusted mean change from baseline** | -1.52 | -1.09
Estimated treatment difference [95%CI]; Insulin Degludec - Sitagliptin | -0.43 [-0.61;-0.24]^1
Proportion Achieving HbA1c < 7% at Trial End | 40.9% | 27.9%
FPG (mg/dL)
Baseline | 170 | 179
End of trial | 112 | 154
Adjusted mean change from baseline | -61.4 | -22.3
Daily insulin dose
Baseline mean | 10 U | N/A
Mean dose after 26 weeks | 43 U | N/A

*OAD: oral antidiabetic agent
**The change from baseline to end of treatment visit in HbA1c was analyzed using ANOVA with treatment, region, sex, and anti-diabetic treatment at screening as fixed effects, and age and baseline HbA1c as covariates.
In Study I, there were 20.9% of subjects in the Insulin Degludec and 22.5% Sitagliptin arms for whom data was missing at the time of the HbA1c measurement.
^1p <0.001; 1-sided p-value evaluated at 2.5% level for superiority

14.4 Safety Outcomes Trial

DEVOTE (NCT01959529) Cardiovascular Outcomes Trial of Insulin Degludec Administered Once-Daily Between Dinner and Bedtime in Combination with Standard of Care in Subjects with Type 2 Diabetes and Atherosclerotic Cardiovascular Disease

DEVOTE was a multi-center, multi-national, randomized, double-blinded, active-controlled, treat-to-target, event-driven trial. 7,637 patients with inadequately controlled type 2 diabetes and atherosclerotic cardiovascular disease were randomized to either Insulin Degludec or insulin glargine U-100. Each was administered once-daily between dinner and bedtime in addition to standard of care for diabetes and cardiovascular disease for a median duration of 2 years.

Patients eligible to enter the trial were; 50 years of age or older and had established, stable, cardiovascular, cerebrovascular, peripheral artery disease, chronic kidney disease or NYHA class II and III heart failure (85% of the enrolled population) or were 60 years of age or older and had other specified risk factors for cardiovascular disease (15% of the enrolled population).

At baseline, demographic and disease characteristics were balanced between treatment groups. The mean age of the trial population was 65 years and the mean duration of diabetes was 16 years. The population was 63% male, 76% White 11% Black or African American, 10% Asian. 15% had Hispanic ethnicity. The mean HbA1c was 8.4% and the mean BMI was 33.6 kg/m^2. The baseline mean estimated glomerular filtration rate (eGFR) was 68 mL/min/1.73m^2. 41% of patients had eGFR 60-90 mL/min/1.73m^2; 35% of patients had eGFR 30 to 60 mL/min/1.73 m^2 and 3% of patients had eGFR <30 mL/min/1.73 m^2. Previous history of severe hypoglycemia was not captured in the trial.

At baseline, patients treated their diabetes with oral antidiabetic drugs (72%) and with an insulin regimen (84%). Types of insulins included long acting insulin (60%), intermediate acting insulin (14%) short acting insulin (37%) and premixed insulin (10%). 16% of patients were insulin naive. The most common background oral antidiabetic drugs used at baseline were metformin (60%), sulfonylureas (29%) and DPP-4 inhibitors (12%).

During the trial, investigators could modify anti-diabetic and cardiovascular medications to achieve local standard of care treatment targets for lipids and blood pressure.

Cardiovascular Outcomes - Patients with T2DM and Atherosclerotic CVD

The incidence of major cardiovascular events with Insulin Degludec was evaluated in DEVOTE. Subjects treated with Insulin Degludec had a similar incidence of major adverse cardiovascular events (MACE) when compared to those treated with insulin glargine U-100.

The primary endpoint in DEVOTE was time from randomization to the first occurrence of a 3-component major adverse cardiovascular event (MACE): cardiovascular death, non-fatal myocardial infarction, or non-fatal stroke. The trial was designed to exclude a pre-specified risk margin of 1.3 for the hazard ratio of MACE comparing Insulin Degludec to insulin glargine U-100. The primary outcome at end of trial was available for 98.2% of participants in each treatment group.

The time to first occurrence of MACE with Insulin Degludec as compared to insulin glargine U-100 was non-inferior (HR: 0.91; 95% CI [0.78;1.06]; see Figure 3). The results of the primary composite MACE endpoint and a summary of its individual components are shown in Table 15.

Table 15: Analysis of the Composite 3-point MACE and Individual Cardiovascular Endpoints in DEVOTE

 | Insulin Degludec |  | Insulin glargine U-100
N | 3,818 |  | 3,819
 | Number of Patients (%) | Rate per 100 PYO* | Number of Patients (%) | Rate per 100 PYO* | Hazard Ratio; (95% CI)
Composite of first event of CV death, non-fatal MI, or non-fatal stroke (3-Point MACE) | 325 (8.5) | 4.41 | 356 (9.3) | 4.86 | 0.91; [0.78; 1.06]
CV death | 136 (3.6) | 1.85 | 142 (3.7) | 1.94
Non-fatal MI | 144 (3.8) | 1.95 | 169 (4.4) | 2.31
Non-fatal stroke | 71 (1.9) | 0.96 | 79 (2.1) | 1.08

* PYO = patient-years of observation until first MACE, death, or trial discontinuation

Figure 3: Cumulative Event Probability for Time to First MACE in DEVOTE

Hypoglycemia Outcomes - Patients with T2DM and Atherosclerotic CVD

The pre-specified secondary endpoints of event and incidence rates of severe hypoglycemia were sequentially tested.

Severe hypoglycemia was defined as an episode requiring assistance of another person to actively administer carbohydrate, glucagon, or other resuscitative actions and during which plasma glucose concentration may not have been available, but where neurological recovery following the return of plasma glucose to normal was considered sufficient evidence that the event was induced by a low plasma glucose concentration.

The incidence of severe hypoglycemia was lower in the Insulin Degludec group as compared to the insulin glargine U-100 group (Table 16). Glycemic control between the two groups was similar at baseline and throughout the trial.

Table 16: Severe Hypoglycemic Episodes in Patients Treated with Insulin Degludec or Insulin Glargine U-100 in DEVOTE

 | Insulin Degludec | Insulin glargine U-100
N | 3,818 | 3,819
Severe Hypoglycemia
Percent of patients with events | 4.9% | 6.6%
Estimated odds ratio [95%CI] Insulin Degludec/Insulin glargine U-100 | 0.73 [0.60; 0.89]*
Events per 100 Patient Years of Observation | 3.70 | 6.25
Estimated rate ratio [95%CI] Insulin Degludec/Insulin glargine U-100 | 0.60 [0.48; 0.76]*

* Test for superiority evaluated at 5% level for significance, (2-sided p<0.001)

16 HOW SUPPLIED/STORAGE AND HANDLING

Product: 50090-7176

NDC: 50090-7176-0 3 mL in a SYRINGE, PLASTIC / 5 in a CARTON

17 PATIENT COUNSELING INFORMATION

Advise the patient and/or caregiver to read the FDA-approved patient labeling (Patient Information and Instructions for Use). There are separate Instructions for Use for the Vials and FlexTouch Pens.

Never Share an Insulin Degludec FlexTouch Pen, Needle, or Insulin Syringe Between Patients

Advise patients that they should never share an Insulin Degludec FlexTouch pen device with another person, even if the needle is changed. Advise patients using Insulin Degludec vials not to share needles or insulin syringes with another person. Sharing poses a risk for transmission of blood-borne pathogens [see Warnings and Precautions (5.1)].

Hyperglycemia or Hypoglycemia

Inform patients that hypoglycemia is the most common adverse reaction with insulin. Inform patients of the symptoms of hypoglycemia (e.g., impaired ability to concentrate and react). This may present a risk in situations where these abilities are especially important, such as driving or operating other machinery. Advise patients who have frequent hypoglycemia or reduced or absent warning signs of hypoglycemia to use caution when driving or operating machinery [see Warnings and Precautions (5.3)].

Advise patients that changes in insulin regimen can predispose to hyperglycemia or hypoglycemia and that changes in insulin regimen should be made under close medical supervision [see Warnings and Precautions (5.2)].

Hypoglycemia Due to Medication Errors

Inform patients to always check the insulin label before each injection to reduce the risk of a medication error [see Warnings and Precautions (5.4)]. Inform patients that the dose counter of Insulin Degludec FlexTouch pen shows the number of units of Insulin Degludec to be injected. NO dose re-calculation is required [see Dosage and Administration (2.2)]. Instruct patients to never use a syringe to remove Insulin Degludec from the FlexTouch disposable insulin prefilled pen.

Hypersensitivity Reactions

Advise patients that hypersensitivity reactions have occurred with Insulin Degludec. Inform patients on the symptoms of hypersensitivity reactions [see Warnings and Precautions (5.5)].

Version: 1

Novo Nordisk®, FlexTouch®, LEVEMIR®, NOVOLOG®, and NovoFine® are registered trademarks of Novo Nordisk A/S.

© 2022 Novo Nordisk

PATENT Information: http://novonordisk-us.com/products/product-patents.html

Manufactured by:

Novo Nordisk Inc.

800 Scudders Mill Road

Plainsboro, NJ 08536

U.S. License Number 1261

For information about Insulin Degludec contact:

Novo Nordisk Pharma, Inc.

1-800-727-6500

PATIENT INFORMATION

Insulin Degludec

injection, for subcutaneous use

This product is Tresiba (insulin degludec).

Do not share your Insulin Degludec FlexTouch insulin delivery device with other people, even if the needle has changed. Do not share needles or syringes with another person. You may give other people a serious infection, or get a serious infection from them.

What is Insulin Degludec?

- Insulin Degludec is a man-made insulin that is used to control high blood sugar in adults and children who are 1 year of age and older with diabetes mellitus.
- Insulin Degludec is not for people with diabetic ketoacidosis (increased ketones in the blood or urine).
- It is not known if Insulin Degludec is safe and effective in children under 1 year of age.
- Insulin Degludec is available in 2 concentrations (U-100 and U-200):
  - U-100 concentration is available in pen and vial
    - The 100 units/mL pen can be injected from 1 to 80 units in a single injection, in increments of 1 unit.
    - The 100 units/mL vial should be used with a U-100 insulin syringe only.
  - U-200 concentration is only available in pen
    - The 200 units/mL pen can be injected from 2 to 160 units in a single injection, in increments of 2 units.

Who should not take Insulin Degludec?

Do not take Insulin Degludec if you:

- are having an episode of low blood sugar (hypoglycemia).
- have an allergy to Insulin Degludec or any of the ingredients in Insulin Degludec.

Before taking Insulin Degludec, tell your healthcare provider about all your medical conditions including, if you are:

- pregnant, planning to become pregnant, or are breastfeeding.
- taking new prescription or over-the-counter medicines, vitamins, or herbal supplements.

Before you start taking Insulin Degludec, talk to your healthcare provider about low blood sugar and how to manage it.

How should I take Insulin Degludec?

- Read the Instructions for Use that come with your Insulin Degludec.
- Take Insulin Degludec exactly as your healthcare provider tells you to.
- Do not do any conversion of your dose. The dose counter always shows the selected dose in units. Both the 100 units/mL and 200 units/mL Insulin Degludec FlexTouch pens are made to deliver your insulin dose in units.
- Know the type and strength of insulin you take. Do not change the type of insulin you take unless your healthcare provider tells you to. The amount of insulin and the best time for you to take your insulin may need to change if you take different types of insulin.
- For children who need less than 5 units of Insulin Degludec each day, use a Insulin Degludec U-100 vial.
- Adults: If you miss or are delayed in taking your dose of Insulin Degludec:
  - Take your dose as soon as you remember then continue with your regular dosing schedule.
  - Make sure there are at least 8 hours between your doses.
- If children miss a dose of Insulin Degludec:
  - Call the healthcare provider for information and instructions about checking blood sugar levels more often until the next scheduled dose of Insulin Degludec.
- Check your blood sugar levels. Ask your healthcare provider what your blood sugars should be and when you should check your blood sugar levels.
- Do not reuse or share your needles with other people. You may give other people a serious infection or get a serious infection from them.
- Never inject Insulin Degludec into a vein or muscle.
- Never use a syringe to remove Insulin Degludec from the FlexTouch pen.
- Insulin Degludec can be injected under the skin (subcutaneously) of your upper legs (thighs), upper arms, or stomach area (abdomen).
- Change (rotate) your injection sites within the area you choose with each dose to reduce your risk of getting lipodystrophy (pits in skin or thickened skin) and localized cutaneous amyloidosis (skin with lumps) at the injection sites.
  - Do not use the exact same spot for each injection.
  - Do not inject where the skin has pits, is thickened, or has lumps.
  - Do not inject where the skin is tender, bruised, scaly or hard, or into scars or damaged skin.

What should I avoid while taking Insulin Degludec?

While taking Insulin Degludec do not:

- Drive or operate heavy machinery, until you know how Insulin Degludec affects you.
- Drink alcohol or use prescription or over-the-counter medicines that contain alcohol.

What are the possible side effects of Insulin Degludec?

Insulin Degludec may cause serious side effects that can lead to death, including:

- Low blood sugar (hypoglycemia). Signs and symptoms that may indicate low blood sugar include:
- dizziness or light-headedness
- blurred vision
- anxiety, irritability, or mood changes
- sweating
- slurred speech
- hunger
- confusion
- shakiness
- headache
- fast heartbeat
- Low potassium in your blood (hypokalemia).
- Heart failure. Taking certain diabetes pills called thiazolidinediones or “TZDs” with Insulin Degludec may cause heart failure in some people. This can happen even if you have never had heart failure or heart problems before. If you already have heart failure, it may get worse while you take TZDs with Insulin Degludec. Your healthcare provider should monitor you closely while you are taking TZDs with Insulin Degludec. Tell your healthcare provider if you have any new or worse symptoms of heart failure including shortness of breath, tiredness, swelling of your ankles or feet and sudden weight gain. Treatment with TZDs and Insulin Degludec may need to be adjusted or stopped by your healthcare provider if you have new or worse heart failure.

Your insulin dose may need to change because of:

- change in level of physical activity or exercise
- weight gain or loss
- increased stress
- illness
- change in diet

Common side effects of Insulin Degludec may include:

- serious allergic reactions (whole body reactions), reactions at the injection site, skin thickening or pits at the injection site (lipodystrophy), itching, rash, swelling of your hands and feet, and weight gain.

Get emergency medical help if you have:

- trouble breathing, shortness of breath, fast heartbeat, swelling of your face, tongue, or throat, sweating, extreme drowsiness, dizziness, confusion.

These are not all the possible side effects of Insulin Degludec. Call your doctor for medical advice about side effects. You may report side effects to FDA at 1-800-FDA-1088.

General information about the safe and effective use of Insulin Degludec.

Medicines are sometimes prescribed for purposes other than those listed in a Patient Information leaflet. You can ask your pharmacist or healthcare provider for information about Insulin Degludec that is written for health professionals. Do not use Insulin Degludec for a condition for which it was not prescribed. Do not give Insulin Degludec to other people, even if they have the same symptoms that you have. It may harm them.

What are the ingredients in Insulin Degludec?

Active Ingredient: insulin degludec

Inactive Ingredients: glycerin, metacresol, phenol, zinc, and Water for Injection, USP. Hydrochloric acid or sodium hydroxide may be added.

Manufactured by:
Novo Nordisk Inc., Plainsboro, NJ 08536, U.S. License Number 1261

For more information call 1-800-727-6500.

This Patient Information has been approved by the U.S. Food and Drug Administration.

Revised: 07/2022

INSTRUCTIONS FOR USE

INSTRUCTIONS FOR USE

Insulin Degludec

injection, for subcutaneous use

10 mL multiple-dose vial (100 units/mL, U-100)

This product is Tresiba (insulin degludec).

Read this Instructions for Use before you start taking Insulin Degludec and each time you get a refill. There may be new information. This information does not take the place of talking to your healthcare provider about your medical condition or your treatment.

The vial is not recommended for use by the blind or visually impaired without the assistance of a person trained in the proper use of the product and insulin syringe.

Do not reuse or share syringes or needles with other people. You may give other people a serious infection or get a serious infection from them.

Supplies you will need to give your Insulin Degludec injection:

- a 10 mL Insulin Degludec vial
- a U-100 insulin syringe and needle
- 2 alcohol swabs
- 1 sharps container for throwing away used syringes and needles. See “Disposing of your used needles and syringes” at the end of these instructions.

Preparing your Insulin Degludec dose:

- Do not roll or shake the Insulin Degludec vial. Shaking the Insulin Degludec vial right before the dose is drawn into the syringe may cause bubbles or foam. This can cause you to draw up the wrong dose of insulin.
- The tamper-resistant cap should not be loose or damaged before the first use. Do not use if the tamper-resistant cap is loose or damaged before using Insulin Degludec for the first time.
- Wash your hands with soap and water.
- Before you start to prepare your injection, check the Insulin Degludec label to make sure that you are taking the right type of insulin. This is especially important if you use more than 1 type of insulin.
- Check that the Insulin Degludec vial is not cracked or damaged. Do not use if the Insulin Degludec vial is cracked or damaged.
- Insulin Degludec should look clear and colorless. Do not use Insulin Degludec if it is thick, cloudy, or is colored.
- Do not use Insulin Degludec past the expiration date printed on the label or 56 days after you start using the Insulin Degludec vial.

Step 1: Pull off the tamper-resistant cap (See Figure A).

Step 2: Wipe the rubber stopper with an alcohol swab (See Figure B).

(Figure A Figure B)

Step 3: Hold the syringe with the needle pointing up. Pull down on the plunger until the tip of the plunger reaches the line for the number of units for your prescribed dose (See Figure C).

(Figure C)

Step 4: Push the needle through the rubber stopper of the Insulin Degludec vial (See Figure D).

(Figure D)

Step 5: Push the plunger all the way in. This puts air into the Insulin Degludec vial (See Figure E).

(Figure E)

Step 6: Turn the Insulin Degludec vial and syringe upside down and slowly pull the plunger down until the tip of the plunger is a few units past the line for your dose (See Figure F).

If there are air bubbles, tap the syringe gently a few times to let any air bubbles rise to the top (See Figure G).

(Figure F)

(Figure G)

Step 7: Slowly push the plunger up until the tip of the plunger reaches the line for your prescribed Insulin Degludec dose (See Figure H).

(Figure H)

Step 8: Check the syringe to make sure you have the right dose of Insulin Degludec.

Step 9: Pull the syringe out of the rubber stopper on the Insulin Degludec vial (See Figure I).

(Figure I)

Giving your Insulin Degludec injection:
2. Inject your Insulin Degludec exactly as your healthcare provider has shown you. Your healthcare provider should tell you if you need to pinch the skin before injecting.
3. Insulin Degludec can be injected under the skin (subcutaneously) of your upper legs (thighs), upper arms, or stomach area (abdomen). Do not inject Insulin Degludec into your muscle.
4. Change (rotate) your injection sites within the area you choose for each dose to reduce your risk of getting
lipodystrophy (pits in skin or thickened skin) and localized cutaneous amyloidosis (skin with lumps) at the injection
sites. Do not use the same injection site for each injection. Do not inject where the skin has pits, is thickened, or has
lumps. Do not inject where the skin is tender, bruised, scaly or hard, or into scars or damaged skin.
8. Do not dilute or mix Insulin Degludec with any other type of insulin or solutions.

Step 10: Choose your injection site (thighs, upper arms, or abdomen) and wipe the skin with an alcohol swab (See Figure J).

Let the injection site dry before you inject your dose.

(Figure J)

Step 11: Insert the needle into your skin. Push down on the plunger to inject your dose (See Figure K).

Make sure you have injected all the insulin in the syringe.

(Figure K)

Step 12: Pull the needle out of your skin. After your injection, you may see a drop of Insulin Degludec at the needle tip.

This is normal and does not affect the dose you just received (See Figure L).

- If you see blood after you take the needle out of your skin, press the injection site lightly with a piece of gauze or an alcohol swab. Do not rub the area.

(Figure L)

After your injection:

- Do not recap the needle. Recapping the needle can lead to needle stick injury.

Disposing of your used needles and syringes:

Put your used insulin needles and syringes in a FDA-cleared sharps disposal container right away after use. Do not throw away (dispose of) loose needles and syringes in your household trash.

If you do not have a FDA-cleared sharps disposal container, you may use a household container that is:

  - made of a heavy-duty plastic
  - can be closed with a tight-fitting, puncture-resistant lid, without sharps being able to come out
  - upright and stable during use
  - leak-resistant
  - properly labeled to warn of hazardous waste inside the container.
- When your sharps disposal container is almost full, you will need to follow your community guidelines for the right way to dispose of your sharps disposal container. There may be state or local laws about how you should throw away used needles and syringes. Do not reuse or share needles or syringes with another person. For more information about safe sharps disposal, and for specific information about sharps disposal in the state that you live in, go to the FDA’s website at: http://www.fda.gov/safesharpsdisposal.
- Do not dispose of your used sharps disposal container in your household trash unless your community guidelines permit this. Do not recycle your used sharps disposal container.

How should I store Insulin Degludec?

Before use:

- Store unopened Insulin Degludec vials in the refrigerator at 36°F to 46°F (2°C to 8°C) in the original carton to protect from light.
- Do not freeze Insulin Degludec. Do not use Insulin Degludec if it has been frozen.
- Unused Insulin Degludec vials may be used until the expiration date printed on the label, if they are kept in the refrigerator.
- After 56 days, throw away Insulin Degludec vials that have been kept at room temperature (up to 86°F (30°C)).

Vial in use:

- Store the Insulin Degludec vial you are currently using in the refrigerator between 36°F to 46°F (2°C to 8°C) or keep at room temperature up to 86°F (30°C) in the original carton to protect from light.
- Keep Insulin Degludec away from direct heat or light.
- The Insulin Degludec vial you are using should be thrown away after 56 days, even if it still has insulin left in it and the expiration date has not passed.

General information about the safe and effective use of Insulin Degludec

- Keep Insulin Degludec vials, syringes, and needles out of the reach of children.
- Always use a new syringe and needle for each injection to help ensure sterility and prevent blocked needles.
- Do not reuse or share syringes or needles with other people. You may give other people a serious infection or get a serious infection from them.

This Instructions for Use has been approved by the U.S. Food and Drug Administration.

Manufactured by:

Novo Nordisk Inc.

800 Scudders Mill Road

Plainsboro, NJ 08536

U.S. License Number 1261

Novo Nordisk® is a registered trademark of Novo Nordisk A/S.

Patent Information:

http://novonordisk-us.com/products/product-patents.html

Revised: 07/2022

© 2022 Novo Nordisk

For information contact:

Novo Nordisk Pharma, Inc.

1-800-727-6500

(Se habla español)

Read before first use

INSTRUCTIONS FOR USE

Insulin Degludec

injection, for subcutaneous use

FlexTouch® Pen 100 units/mL

This product is Tresiba (insulin degludec).

Please read the following instructions carefully before using your Insulin Degludec FlexTouch Pen.

- Do not share your Insulin Degludec FlexTouch Pen with other people, even if the needle is changed. You may give other people a serious infection, or get a serious infection from them.
- Insulin Degludec FlexTouch Pen 100 units/mL (“Pen”) is a prefilled disposable, single-patient-use insulin pen containing 300 units of insulin degludec. You can inject from 1 to 80 units in a single injection. The units can be increased by 1 unit at a time.
- This Pen is not recommended for use by the blind or visually impaired without the assistance of a person trained in the proper use of the product.

Supplies you will need to give your Insulin Degludec injection:

- Insulin Degludec FlexTouch Pen
- a new NovoFine or NovoTwist needle
- alcohol swab
- a sharps container for throwing away used Pens and needles. See “After your injection” at the end of these instructions.

Preparing your Insulin Degludec FlexTouch Pen:

- Wash your hands with soap and water.
- Before you start to prepare your injection, check the Insulin Degludec FlexTouch Pen label to make sure you are taking the right type of insulin. This is especially important if you take more than 1 type of insulin.
- Insulin Degludec should look clear and colorless. Do not use Insulin Degludec if it is cloudy or colored.
- Do not use Insulin Degludec past the expiration date printed on the label or 56 days after you start using the Pen.
- Always use a new needle for each injection to help ensure sterility and prevent blocked needles. Do not reuse or share needles with another person. You may give other people a serious infection, or get a serious infection from them.

Step 1:

- Pull Pen cap straight off (See Figure B).

Step 2:

- Check the liquid in the Pen (See Figure C). Insulin Degludec should look clear and colorless. Do not use it if it looks cloudy or colored.

Step 3:

- Select a new needle.
- Pull off the paper tab from the outer needle cap (See Figure D).

Step 4:

- Push the capped needle straight onto the Pen and twist the needle on until it is tight (See Figure E).

Step 5:

- Pull off the outer needle cap. Do not throw it away (See Figure F).

Step 6:

- Pull off the inner needle cap and throw it away (See Figure G).

Priming your Insulin Degludec FlexTouch Pen:

Step 7:

- Turn the dose selector to select 2 units (See Figure H).

Step 8:

- Hold the Pen with the needle pointing up. Tap the top of the Pen gently a few times to let any air bubbles rise to the top (See Figure I).

Step 9:

- Hold the Pen with the needle pointing up. Press and hold in the dose button until the dose counter shows “0”. The “0” must line up with the dose pointer.
- A drop of insulin should be seen at the needle tip (See Figure J).
- If you do not see a drop of insulin, repeat steps 7 to 9, no more than 6 times.
- If you still do not see a drop of insulin, change the needle and repeat steps 7 to 9.

Selecting your dose:

Step 10:

Insulin Degludec FlexTouch Pen 100 units/mL is made to deliver the number of insulin units that your healthcare provider prescribed. Do not perform any dose conversion.

Check to make sure the dose selector is set at 0.

- Turn the dose selector to select the number of units you need to inject. The dose pointer should line up

with your dose (See Figure K).

- If you select the wrong dose, you can turn the dose selector forwards or backwards to the correct dose.
- The even numbers are printed on the dial.
- The odd numbers are shown as lines.

- The Insulin Degludec FlexTouch Pen insulin scale will show you how much insulin is left in your Pen (See Figure L).

- To see how much insulin is left in your Insulin Degludec FlexTouch Pen:
- Turn the dose selector until it stops. The dose counter will line up with the number of units of insulin that is left in your Pen. If the dose counter shows 80, there are at least 80 units left in your Pen.
- If the dose counter shows less than 80, the number shown in the dose counter is the number of units left in your Pen.

Giving your injection:

- Inject your Insulin Degludec exactly as your healthcare provider has shown you. Your healthcare provider should tell you if you need to pinch the skin before injecting.
- Insulin Degludec can be injected under the skin (subcutaneously) of your upper legs (thighs), upper arms, or stomach area (abdomen).
- Change (rotate) your injection sites within the area you choose for each dose to reduce your risk of getting lipodystrophy (pits in skin or thickened skin) and localized cutaneous amyloidosis (skin with lumps) at the injection sites. Do not use the same injection site for each injection. Do not inject where the skin has pits, is thickened, or has lumps. Do not inject where the skin is tender, bruised, scaly or hard, or into scars or damaged skin.

Step 11:

- Choose your injection site (thighs, upper arms, or abdomen) and wipe the skin with an alcohol swab (See Figure M). Let the injection site dry before you inject your dose.

Step 12:

- Insert the needle into your skin (See Figure N).
- Make sure you can see the dose counter. Do not cover it with your fingers, this can stop your injection.

Step 13:

- Press and hold down the dose button until the dose counter shows “0” (See Figure O).
- The “0” must line up with the dose pointer. You may then hear or feel a click.

- Keep the needle in your skin after the dose counter has returned to “0” and slowly count to 6 (See Figure P).
- When the dose counter returns to “0”, you will not get your full dose until 6 seconds later.
- If the needle is removed before you count to 6, you may see a stream of insulin coming from the needle tip.
- If you see a stream of insulin coming from the needle tip you will not get your full dose. If this happens you should check your blood sugar levels more often because you may need more insulin.

Step 14:

- Pull the needle out of your skin (See Figure Q).
- If you see blood after you take the needle out of your skin, press the injection site lightly with a piece of gauze or an alcohol swab. Do not rub the area.

Step 15:

- Carefully remove the needle from the Pen and throw it away (See Figure R).
- Do not recap the needle. Recapping the needle can lead to needle stick injury.

- If you do not have a sharps container, carefully slip the needle into the outer needle cap (See Figure S). Safely remove the needle and throw it away as soon as you can.

- Do not store the Pen with the needle attached. Storing without the needle attached helps prevent leaking, blocking of the needle, and air from entering the Pen.

Step 16:

- Replace the Pen cap by pushing it straight on (See Figure T).

After your injection:

- The used Insulin Degludec FlexTouch Pen may be thrown away in your household trash after you have removed the needle.
- Put your used needles in a FDA-cleared sharps disposal container right away after use. Do not throw away (dispose of) loose needles in your household trash.
- If you do not have a FDA-cleared sharps disposal container, you may use a household container that is:
  - made of a heavy-duty plastic
  - can be closed with a tight-fitting, puncture-resistant lid, without sharps being able to come out
  - upright and stable during use
  - leak-resistant
  - properly labeled to warn of hazardous waste inside the container
- When your sharps disposal container is almost full, you will need to follow your community guidelines for the right way to dispose of your sharps disposal container. There may be state or local laws about how you should throw away used needles and syringes. Do not reuse or share needles or syringes with another person. For more information about the safe sharps disposal, and for specific information about sharps disposal in the state that you live in, go to the FDA’s website at: http://www.fda.gov/safesharpsdisposal.
- Do not dispose of your used sharps disposal container in your household trash unless your community guidelines permit this. Do not recycle your used sharps disposal container.

How should I store my Insulin Degludec FlexTouch Pen?

Before use:

- Store unused Insulin Degludec FlexTouch Pens in the refrigerator at 36°F to 46°F (2°C to 8°C).
- Do not freeze Insulin Degludec. Do not use Insulin Degludec if it has been frozen.
- Unused Pens may be used until the expiration date printed on the label, if kept in the refrigerator.

Pen in use:

- Store the Pen you are currently using in the refrigerator between 36°F to 46°F (2°C to 8°C) or keep at room temperature up to 86°F (30°C).
- Keep Insulin Degludec away from heat or light.
- The Insulin Degludec FlexTouch Pen you are using should be thrown away after 56 days if it is refrigerated or kept at room temperature, even if it still has insulin left in it and the expiration date has not passed.

General Information about the safe and effective use of Insulin Degludec.

- Keep Insulin Degludec FlexTouch Pens and needles out of the reach of children.
- Always use a new needle for each injection.
- Do not share Insulin Degludec FlexTouch Pens or needles with other people. You may give other people a serious infection, or get a serious infection from them.

This Instructions for Use has been approved by the U.S. Food and Drug Administration.

Manufactured by:
Novo Nordisk Inc.

800 Scudders Mill Road

Plainsboro, NJ 08536

U.S. License Number 1261

For information contact:

Novo Nordisk Pharma, Inc.

1-800-727-6500 (Se habla español)

Revised: 07/2022

© 2022 Novo Nordisk

INSTRUCTIONS FOR USE

Insulin Degludec

injection, for subcutaneous use

FlexTouch® Pen 200 units/mL

This product is Tresiba (insulin degludec).

Please read the following instructions carefully before using your Insulin Degludec FlexTouch Pen.

- Do not share your Insulin Degludec FlexTouch Pen with other people, even if the needle is changed. You may give other people a serious infection, or get a serious infection from them.
- Insulin Degludec FlexTouch Pen 200 units/mL (“Pen”) is a prefilled disposable, single-patient-use insulin pen containing 600 units of insulin degludec. You can inject from 2 to 160 units in a single injection. The units can be increased by 2 units at a time.
- Do not use a syringe to remove insulin from your Pen. If you do, you will get too many units of insulin because the scale on most syringes is for measuring U-100 insulin doses only.
- This Pen is not recommended for use by the blind or visually impaired without the assistance of a person trained in the proper use of the product.

Supplies you will need to give your Insulin Degludec injection:

- Insulin Degludec FlexTouch Pen
- a new NovoFine or NovoTwist needle
- alcohol swab
- a sharps container for throwing away used Pens and needles. See “After your injection” at the end of these instructions.

Preparing your Insulin Degludec FlexTouch Pen:

- Wash your hands with soap and water.
- Before you start to prepare your injection, check the Insulin Degludec FlexTouch Pen label to make sure you are taking the right type of insulin. This is especially important if you take more than 1 type of insulin.
- Insulin Degludec should look clear and colorless. Do not use Insulin Degludec if it is cloudy or colored.
- Do not use Insulin Degludec past the expiration date printed on the label or 56 days after you start using the Pen.
- Always use a new needle for each injection to help ensure sterility and prevent blocked needles. Do not reuse or share needles with another person. You may give other people a serious infection, or get a serious infection from them.

(Figure A)

Step 1:

- Pull Pen cap straight off (See Figure B).

Step 2:

- Check the liquid in the Pen (See Figure C). Insulin Degludec should look clear and colorless. Do not use it if it looks cloudy or colored.

Step 3:

- Select a new needle.
- Pull off the paper tab from the outer needle cap (See Figure D).

Step 4:

- Push the capped needle straight onto the Pen and twist the needle on until it is tight (See Figure E).

Step 5:

- Pull off the outer needle cap. Do not throw it away (See Figure F).

Step 6:

- Pull off the inner needle cap and throw it away (See Figure G).

Priming your Insulin Degludec FlexTouch Pen:

Step 7:

- Turn the dose selector to select 2 units (See Figure H).

Step 8:

- Hold the Pen with the needle pointing up. Tap the top of the Pen gently a few times to let any air bubbles rise to the top (See Figure I).

Step 9:

- Hold the Pen with the needle pointing up. Press and hold in the dose button until the dose counter shows “0”. The “0” must line up with the dose pointer.
- A drop of insulin should be seen at the needle tip (See Figure J).
- If you do not see a drop of insulin, repeat steps 7 to 9, no more than 6 times.
- If you still do not see a drop of insulin, change the needle and repeat steps 7 to 9.

Selecting your dose:

Step 10:

Insulin Degludec FlexTouch Pen 200 units/mL is made to deliver the number of insulin units that your healthcare provider prescribed. Do not perform any dose conversion.

Check to make sure the dose selector is set at 0.

- Turn the dose selector to select the number of units you need to inject. The dose pointer should line up

with your dose (See Figure K).

- If you select the wrong dose, you can turn the dose selector forwards or backwards to the correct dose.
- Each line on the dial is an even number.

- The Insulin Degludec FlexTouch Pen insulin scale will show you how much insulin is left in your Pen (See Figure L).

- To see how much insulin is left in your Insulin Degludec FlexTouch Pen:
- Turn the dose selector until it stops. The dose counter will line up with the number of units of insulin that is
  left in your Pen. If the dose counter shows 160, there are at least 160 units left in your Pen.
- If the dose counter shows less than 160, the number shown in the dose counter is the number of units left in your Pen.

Giving your injection:

- Inject your Insulin Degludec exactly as your healthcare provider has shown you. Your healthcare provider should tell you if you need to pinch the skin before injecting.
- Insulin Degludec can be injected under the skin (subcutaneously) of your upper legs (thighs), upper arms, or stomach area (abdomen).
- Change (rotate) your injection sites within the area you choose for each dose to reduce your risk of getting lipodystrophy (pits in skin or thickened skin) and localized cutaneous amyloidosis (skin with lumps) at the injection sites. Do not use the same injection site for each injection. Do not inject where the skin has pits, is thickened, or has lumps. Do not inject where the skin is tender, bruised, scaly or hard, or into scars or damaged skin.

Step 11:

- Choose your injection site (thighs, upper arms, or abdomen) and wipe the skin with an alcohol swab (See Figure M). Let the injection site dry before you inject your dose.

Step 12:

- Insert the needle into your skin (See Figure N).
- Make sure you can see the dose counter. Do not cover it with your fingers, this can stop your injection.

Step 13:

- Press and hold down the dose button until the dose counter shows “0” (See Figure O).
- The “0” must line up with the dose pointer. You may then hear or feel a click.

- Keep the needle in your skin after the dose counter has returned to “0” and slowly count to 6 (See Figure P).
- When the dose counter returns to “0”, you will not get your full dose until 6 seconds later.
- If the needle is removed before you count to 6, you may see a stream of insulin coming from the needle tip.
- If you see a stream of insulin coming from the needle tip you will not get your full dose. If this happens you should check your blood sugar levels more often because you may need more insulin.

Step 14:

- Pullthe needleout of your skin (See Figure Q).
- If you see blood after you take the needle out of your skin, press the injection site lightly with a piece of gauze or an alcohol swab. Do not rub the area.

Step 15:

- Carefully remove the needle from the Pen and throw it away (See Figure R).
- Do not recap the needle. Recapping the needle can lead to needle stick injury.

- If you do not have a sharps container, carefully slip the needle into the outer needle cap (See Figure S). Safely remove the needle and throw it away as soon as you can.

- Do not store the Pen with the needle attached. Storing without the needle attached helps prevent leaking, blocking of the needle, and air from entering the Pen.

Step 16:

- Replace the Pen cap by pushing it straight on (See Figure T).

After your injection:

- The used Insulin Degludec FlexTouch Pen may be thrown away in your household trash after you have removed the needle.
- Put your used needles in a FDA-cleared sharps disposal container right away after use. Do not throw away (dispose of) loose needles in your household trash.
- If you do not have a FDA-cleared sharps disposal container, you may use a household container that is:
- made of a heavy-duty plastic
- can be closed with a tight-fitting, puncture-resistant lid, without sharps being able to come out
- upright and stable during use
- leak-resistant
- properly labeled to warn of hazardous waste inside the container
- When your sharps disposal container is almost full, you will need to follow your community guidelines for the right way to dispose of your sharps disposal container. There may be state or local laws about how you should throw away used needles and syringes. Do not reuse or share needles or syringes with another person. For more information about the safe sharps disposal, and for specific information about sharps disposal in the state that you live in, go to the FDA’s website at: http://www.fda.gov/safesharpsdisposal.
- Do not dispose of your used sharps disposal container in your household trash unless your community guidelines permit this. Do not recycle your used sharps disposal container.

How should I store my Insulin Degludec FlexTouch Pen?

Before use:

- Store unused Insulin Degludec FlexTouch Pens in the refrigerator at 36°F to 46°F (2°C to 8°C).
- Do not freeze Insulin Degludec. Do not use Insulin Degludec if it has been frozen.
- Unused Pens may be used until the expiration date printed on the label, if kept in the refrigerator.

Pen in use:

- Store the Pen you are currently using in the refrigerator between 36°F to 46°F (2°C to 8°C) or keep at room temperature up to 86°F (30°C).
- Keep Insulin Degludec away from heat or light.
- The Insulin Degludec FlexTouch Pen you are using should be thrown away after 56 days if it is refrigerated or kept at room temperature, even if it still has insulin left in it and the expiration date has not passed.

General Information about the safe and effective use of Insulin Degludec.

- Keep Insulin Degludec FlexTouch Pens and needles out of the reach of children.
- Always use a new needle for each injection.
- Do not share Insulin Degludec FlexTouch Pens or needles with other people. You may give other people a serious infection, or get a serious infection from them.

This Instructions for Use has been approved by the U.S. Food and Drug Administration.

Manufactured by:

Novo Nordisk Inc.

800 Scudders Mill Road

Plainsboro, NJ 08536

U.S. License Number 1261

For information contact:
Novo Nordisk Pharma, Inc.
1-800-727-6500 (Se habla español)

Revised: 07/2022

© 2022 Novo Nordisk